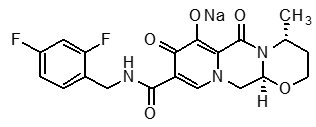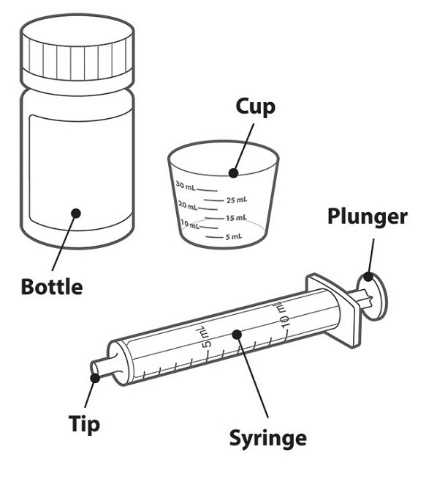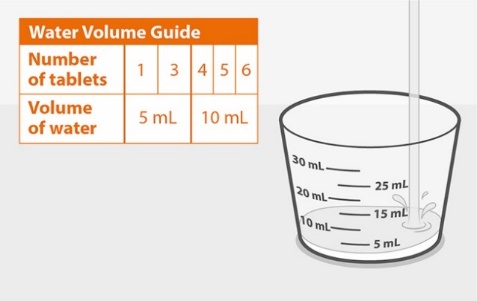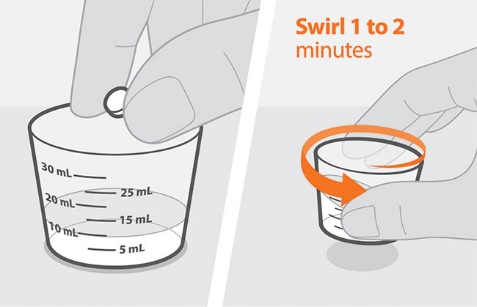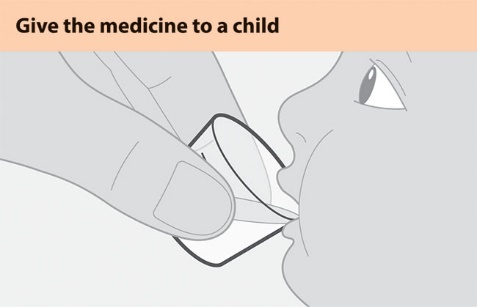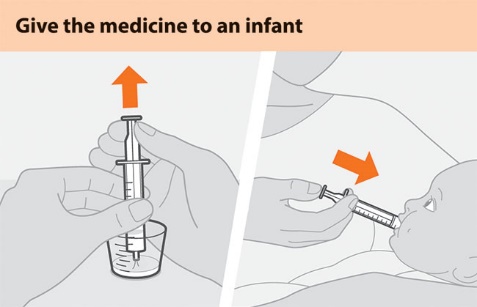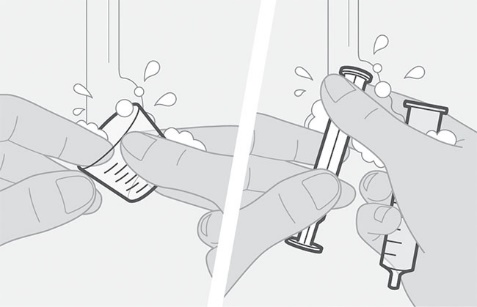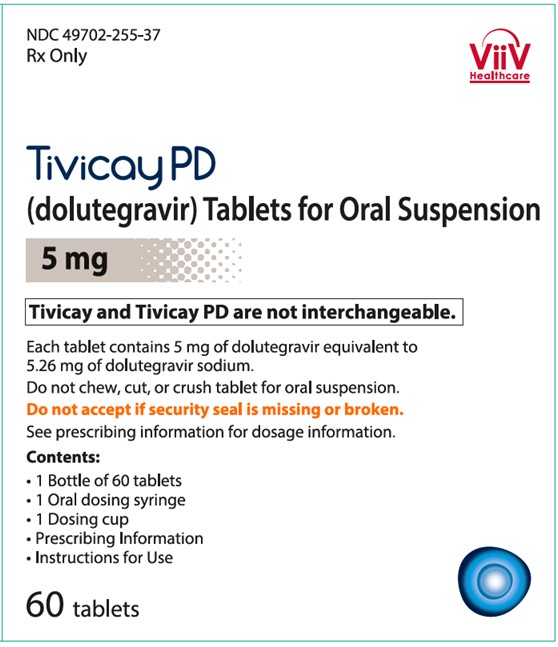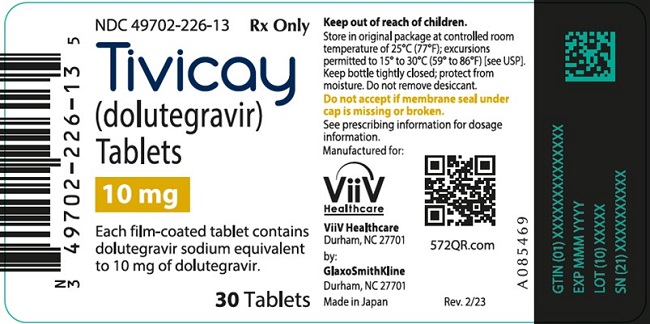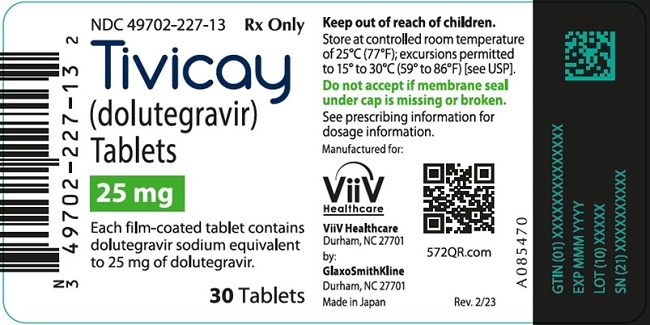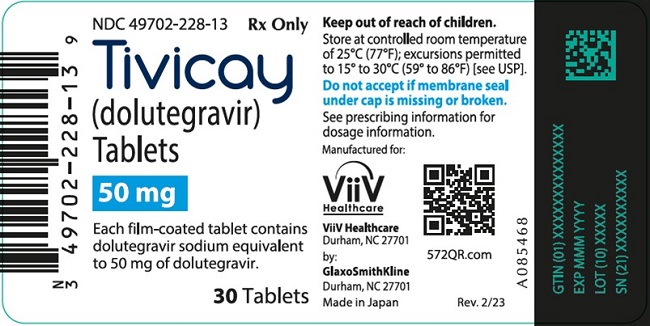 DRUG LABEL: Tivicay PD
NDC: 49702-255 | Form: TABLET, FOR SUSPENSION
Manufacturer: ViiV Healthcare Company
Category: prescription | Type: HUMAN PRESCRIPTION DRUG LABEL
Date: 20251029

ACTIVE INGREDIENTS: DOLUTEGRAVIR SODIUM 5 mg/1 1
INACTIVE INGREDIENTS: CALCIUM SULFATE DIHYDRATE; CROSPOVIDONE, UNSPECIFIED; MANNITOL; MICROCRYSTALLINE CELLULOSE; POVIDONE K30; SODIUM STARCH GLYCOLATE TYPE A CORN; SUCRALOSE; SODIUM STEARYL FUMARATE; HYPROMELLOSE, UNSPECIFIED; POLYETHYLENE GLYCOL, UNSPECIFIED; TITANIUM DIOXIDE

HIGHLIGHTS OF PRESCRIBING INFORMATION

These highlights do not include all the information needed to use TIVICAY safely and effectively. See full prescribing information for TIVICAY.
TIVICAY (dolutegravir) tablets, for oral use
TIVICAY PD (dolutegravir) tablets for oral suspension
Initial U.S. Approval: 2013

1 INDICATIONS AND USAGE

TIVICAY and TIVICAY PD are an HIV-1 integrase strand transfer inhibitor (INSTI) indicated in combination with other antiretroviral agents for the treatment of HIV-1 infection in adults (treatment-naïve or -experienced) and in pediatric patients (treatment-naïve or -experienced but INSTI- naïve) aged at least 4 weeks and weighing at least 3 kg. (1)

TIVICAY is indicated in combination with rilpivirine as a complete regimen for the treatment of HIV-1 infection in adults to replace the current antiretroviral regimen in those who are virologically suppressed (HIV-1 RNA less than 50 copies/mL) on a stable antiretroviral regimen for at least 6 months with no history of treatment failure or known substitutions associated with resistance to either antiretroviral agent. (1)

2 DOSAGE AND ADMINISTRATION

- May be taken without regard to food. (2.2, 2.6)

Adult Population | Recommended Dose
Treatment-naïve or treatment-experienced INSTI-naïve or virologically suppressed (HIV-1 RNA <50 copies per mL) adults switching to dolutegravir plus rilpivirinea (2.1) | 50 mg once daily
Treatment-naïve or treatment-experienced INSTI-naïve when coadministered with certain UGT1A or CYP3A inducers (2.1, 7.2, 7.3) | 50 mg twice daily
INSTI-experienced with certain INSTI-associated resistance substitutions or clinically suspected INSTI resistanceb (2.1, 12.4) | 50 mg twice daily
UGT = uridine diphosphate glucuronosyltransferase; CYP = cytochrome P450.
a Rilpivirine dose is 25 mg once daily for those switching to dolutegravir plus rilpivirine.
b Alternative combinations that do not include metabolic inducers should be considered where possible.

Pediatric Patients: Treatment-naïve or treatment-experienced INSTI-naïve patients aged at least 4 weeks and weighing at least 3 kg. See Tables 2, 3, and 4 for complete pediatric dosing recommendations. (2.3, 2.4, 2.5). TIVICAY and TIVICAY PD are not bioequivalent and are not substitutable on a milligram-per-milligram basis.

Pediatric Population; Body Weight | Recommended Dosea; TIVICAY PD Tablets for Oral Suspension
3 kg to less than 6 kg | 5 mg once daily
6 kg to less than 10 kg | 15 mg once daily
10 kg to less than 14 kg | 20 mg once daily
14 kg to less than 20 kg | 25 mg once daily
20 kg and greater | 30 mg once daily
a If certain UGT1A or CYP3A inducers are coadministered, then adjust the weight-based dose of TIVICAY to twice daily. (2.3, 2.4, 7.2, 7.3)

Alternative dosing recommendations for TIVICAY tablets for patients weighing at least 14 kg (Table 4):

- 14 kg to less than 20 kg: 40 mg once daily.
- 20 kg and greater: 50 mg once daily.

3 DOSAGE FORMS AND STRENGTHS

- TIVICAY tablets: 10 mg, 25 mg, and 50 mg (3)
- TIVICAY PD tablets for oral suspension: 5 mg (3)

4 CONTRAINDICATIONS

- Previous hypersensitivity reaction to dolutegravir. (4)
- Coadministration with dofetilide. (4)

5 WARNINGS AND PRECAUTIONS

- Hypersensitivity reactions characterized by rash, constitutional findings, and sometimes organ dysfunction, including liver injury, have been reported. Discontinue TIVICAY or TIVICAY PD and other suspect agents immediately if signs or symptoms of hypersensitivity reactions develop, as a delay in stopping treatment may result in a life-threatening reaction. (5.1)
- Hepatotoxicity has been reported in patients receiving dolutegravir-containing regimens. Patients with underlying hepatitis B or C may be at increased risk for worsening or development of transaminase elevations. Monitoring for hepatotoxicity is recommended. (5.2)
- Immune reconstitution syndrome has been reported in patients treated with combination antiretroviral therapy. (5.4)
- TIVICAY tablets and TIVICAY PD tablets for oral suspension are not substitutable. (2.2, 5.5)

6 ADVERSE REACTIONS

The most common adverse reactions of moderate to severe intensity and incidence at least 2% (in those receiving TIVICAY in any one adult trial) are insomnia, fatigue, and headache. (6.1)

To report SUSPECTED ADVERSE REACTIONS, contact ViiV Healthcare at 1-877-844-8872 or FDA at 1-800-FDA-1088 or www.fda.gov/medwatch.

7 DRUG INTERACTIONS

- Refer to the full prescribing information for important drug interactions with TIVICAY or TIVICAY PD. (4, 7)
- Drugs that are metabolic inducers may decrease the plasma concentrations of dolutegravir. (7.2, 7.3)
- TIVICAY or TIVICAY PD should be taken 2 hours before or 6 hours after taking cation-containing antacids or laxatives, sucralfate, oral supplements containing iron or calcium, or buffered medications. When taken with food, TIVICAY and supplements containing calcium or iron can be taken at the same time. (7.3)

FULL PRESCRIBING INFORMATION

1 INDICATIONS AND USAGE

TIVICAY and TIVICAY PD are indicated in combination with other antiretroviral agents for the treatment of HIV‑1 infection in adults (treatment-naïve or -experienced) and in pediatric patients (treatment-naïve or -experienced but integrase strand transfer inhibitor [INSTI]-naïve) aged at least 4 weeks and weighing at least 3 kg [see Microbiology (12.4)].

TIVICAY is indicated in combination with rilpivirine as a complete regimen for the treatment of HIV-1 infection in adults to replace the current antiretroviral regimen in those who are virologically suppressed (HIV-1 RNA less than 50 copies/ mL) on a stable antiretroviral regimen for at least 6 months with no history of treatment failure or known substitutions associated with resistance to either antiretroviral agent.

2 DOSAGE AND ADMINISTRATION

2.1 Recommended Dosage in Adults

TIVICAY tablets may be taken with or without food.

Table 1. Dosing Recommendations for TIVICAY Tablets in Adult Patients
Population | Recommended Dosage
Treatment-naïve or treatment-experienced INSTI-naïve or virologically suppressed (HIV‑1 RNA <50 copies/mL) adults switching to dolutegravir plus rilpivirinea | 50 mg once daily
Treatment-naïve or treatment-experienced INSTI-naïve when coadministered with certain uridine diphosphate (UDP)-glucuronosyl transferase 1A1 (UGT1A) or cytochrome P450 (CYP)3A inducers [see Drug Interactions (7.2, 7.3)] | 50 mg twice daily
INSTI-experienced with certain INSTI-associated resistance substitutions or clinically suspected INSTI resistanceb [see Microbiology (12.4)] | 50 mg twice daily
INSTI = integrase strand transfer inhibitor.
a Rilpivirine dose is 25 mg once daily for those switching to dolutegravir plus rilpivirine.
b Alternative combinations that do not include metabolic inducers should be considered where possible [see Drug Interactions (7.3)].

2.2 General Dosing and Administration Instructions for Pediatric Patients

Do not substitute TIVICAY tablets and TIVICAY PD tablets for oral suspension on a milligram-per-milligram basis due to differing pharmacokinetic profiles [see Warnings and Precautions (5.5), Clinical Pharmacology (12.3)]. If switching from the tablets to the tablets for oral suspension, follow the recommended dosage in Table 3. If switching from the tablets for oral suspension to the tablets, follow the recommended dosage in Table 4. See administration instructions in [Dosage and Administration (2.5)].

2.3 Recommended Dosage in Pediatric Patients Weighing 3 to 14 kg

The recommended weight-based dosage of TIVICAY PD tablets for oral suspension in pediatric patients weighing 3 to 14 kg (4 weeks and older, treatment-naïve, or treatment-experienced but naïve to INSTI treatment) is described in Table 2.

Do not use TIVICAY tablets in patients weighing 3 to 14 kg. See administration instructions in [Dosage and Administration (2.5)].

Table 2. Recommended Dosage of TIVICAY PD in Pediatric Patients 4 Weeks and Older Weighing 3 to 14 kg
Body Weight | TIVICAY PD Tablets for Oral Suspension
Body Weight | Daily Dosea | Number of; 5-mg Tablets
3 kg to less than 6 kg | 5 mg once daily | 1
6 kg to less than 10 kg | 15 mg once daily | 3
10 kg to less than 14 kg | 20 mg once daily | 4
a If certain uridine diphosphate glucuronosyltransferase (UGT)1A or cytochrome P450 (CYP)3A inducers are coadministered, then administer TIVICAY PD twice daily [see Drug Interactions (7.2, 7.3)].

2.4 Recommended Dosage in Pediatric Patients Weighing 14 kg or Greater

For pediatric patients weighing 14 kg or greater (4 weeks and older, treatment-naïve, or treatment-experienced but naïve to INSTI treatment) administer either:

- TIVICAY PD tablets for oral suspension (preferred in pediatric patients weighing less than 20 kg) (Table 3), or
- TIVICAY tablets for oral use (Table 4)

Table 3. Recommended Dosage of TIVICAY PD Tablets for Oral Suspension in Pediatric Patients Weighing 14 kg or Greater
Body Weight | TIVICAY PD Tablets for Oral Suspension
Body Weight | Daily Dosea | Number of; 5-mg Tablets
14 kg to less than 20 kg | 25 mg once daily | 5
20 kg and greater | 30 mg once daily | 6
a If certain UGT1A or CYP3A inducers are coadministered, then administer TIVICAY PD twice daily [see Drug Interactions (7.2, 7.3)].

Table 4. Recommended Dosage of TIVICAY Tablets in Pediatric Patients Weighing 14 kg or Greater
Body Weight | TIVICAY Tablets
Body Weight | Daily Dosea | Number of Tablets
14 kg to less than 20 kg | 40 mg once daily | 4 x 10-mg
20 kg and greater | 50 mg once daily | 1 x 50-mg
a If certain UGT1A or CYP3A inducers are coadministered, then administer TIVICAY twice daily [see Drug Interactions (7.2, 7.3)].

2.5 Additional Administration Instructions

Administer TIVICAY tablets and TIVICAY PD tablets for oral suspension with or without food.

Administration Instructions for TIVICAY PD

Do not chew, cut, or crush TIVICAY PD [see Instructions for Use]. Instruct patients (or instruct caregivers) to either:

- Swallow the tablets for oral suspension whole (if more than one tablet is required, swallow one tablet at a time to reduce the risk of choking), or
- Fully disperse the tablets for oral suspension in 5 mL of drinking water (if using 1 or 3 tablets for oral suspension) or 10 mL (if using 4, 5, or 6 tablets for oral suspension) in the supplied cup; swirl the suspension so that no lumps remain. After full dispersion, administer the oral suspension within 30 minutes of mixing [see Instructions for Use].

3 DOSAGE FORMS AND STRENGTHS

TIVICAY Tablets:

10 mg: Each tablet contains 10 mg of dolutegravir (as dolutegravir sodium). Tablets are white, round, film-coated, biconvex tablets debossed with “SV 572” on one side and “10” on the other side.

25 mg: Each tablet contains 25 mg of dolutegravir (as dolutegravir sodium). Tablets are pale yellow, round, film-coated, biconvex tablets debossed with “SV 572” on one side and “25” on the other side.

50 mg: Each tablet contains 50 mg of dolutegravir (as dolutegravir sodium). Tablets are yellow, round, film-coated, biconvex tablets debossed with “SV 572” on one side and “50” on the other side.

TIVICAY PD Tablets for Oral Suspension:

Each tablet contains 5 mg of dolutegravir (as dolutegravir sodium). Tablets are white, round, strawberry cream flavored, film-coated, biconvex tablets debossed with “SV H7S” on one side and “5” on the other side.

4 CONTRAINDICATIONS

TIVICAY and TIVICAY PD are contraindicated in patients:

- with previous hypersensitivity reaction to dolutegravir [see Warnings and Precautions (5.1)].
- receiving dofetilide due to the potential for increased dofetilide plasma concentrations and the risk for serious and/or life-threatening events [see Drug Interactions (7)].

5 WARNINGS AND PRECAUTIONS

5.1 Hypersensitivity Reactions

Hypersensitivity reactions have been reported and were characterized by rash, constitutional findings, and sometimes organ dysfunction, including liver injury. The events were reported in less than 1% of subjects receiving TIVICAY in Phase III clinical trials. Discontinue TIVICAY or TIVICAY PD and other suspect agents immediately if signs or symptoms of hypersensitivity reactions develop (including, but not limited to, severe rash or rash accompanied by fever, general malaise, fatigue, muscle or joint aches, blisters or peeling of the skin, oral blisters or lesions, conjunctivitis, facial edema, hepatitis, eosinophilia, angioedema, difficulty breathing). Clinical status, including liver aminotransferases, should be monitored and appropriate therapy initiated. Delay in stopping treatment with TIVICAY or TIVICAY PD or other suspect agents after the onset of hypersensitivity may result in a life-threatening reaction. TIVICAY and TIVICAY PD are contraindicated in patients who have experienced a previous hypersensitivity reaction to dolutegravir.

5.2 Hepatotoxicity

Hepatic adverse events have been reported in patients receiving a dolutegravir-containing regimen. Patients with underlying hepatitis B or C may be at increased risk for worsening or development of transaminase elevations with use of TIVICAY or TIVICAY PD [see Adverse Reactions (6.1)]. In some cases, the elevations in transaminases were consistent with immune reconstitution syndrome or hepatitis B reactivation particularly in the setting where anti-hepatitis therapy was withdrawn. Cases of hepatic toxicity, including elevated serum liver biochemistries, hepatitis, and acute liver failure have been reported in patients receiving a dolutegravir-containing regimen without pre-existing hepatic disease or other identifiable risk factors. Drug-induced liver injury leading to liver transplant has been reported with TRIUMEQ (abacavir, dolutegravir, and lamivudine). Monitoring for hepatotoxicity is recommended.

5.3 Risk of Adverse Reactions or Loss of Virologic Response Due to Drug Interactions

The concomitant use of TIVICAY or TIVICAY PD and other drugs may result in known or potentially significant drug interactions, some of which may lead to [see Contraindications (4), Drug Interactions (7.3)]:

- Loss of therapeutic effect of TIVICAY or TIVICAY PD and possible development of resistance.
- Possible clinically significant adverse reactions from greater exposures of concomitant drugs.

For concomitant drugs for which the interaction can be mitigated, please see Table 8 for steps to prevent or manage these possible and known significant drug interactions, including dosing recommendations. Consider the potential for drug interactions prior to and during therapy with TIVICAY or TIVICAY PD; review concomitant medications during therapy with TIVICAY or TIVICAY PD; and monitor for the adverse reactions associated with the concomitant drugs.

5.4 Immune Reconstitution Syndrome

Immune reconstitution syndrome has been reported in patients treated with combination antiretroviral therapy, including TIVICAY or TIVICAY PD. During the initial phase of combination antiretroviral treatment, patients whose immune systems respond may develop an inflammatory response to indolent or residual opportunistic infections (such as Mycobacterium avium infection, cytomegalovirus, Pneumocystis jirovecii pneumonia [PCP], or tuberculosis), which may necessitate further evaluation and treatment.

Autoimmune disorders (such as Graves’ disease, polymyositis, and Guillain-Barré syndrome) have also been reported to occur in the setting of immune reconstitution; however, the time to onset is more variable and can occur many months after initiation of treatment.

5.5 Different Formulations Are Not Substitutable

TIVICAY and TIVICAY PD are not bioequivalent and are not substitutable on a milligram-per-milligram basis [see Clinical Pharmacology (12.3)]. If a pediatric patient switches from one formulation to the other, the dose must be adjusted for the new dosage formulation [see Dosage and Administration (2.2)]. Incorrect dosing of a given formulation may result in underdosing and loss of therapeutic effect and possible development of resistance or possible clinically significant adverse reactions from greater exposure of dolutegravir.

6 ADVERSE REACTIONS

The following serious adverse drug reactions are discussed in other sections of the labeling:

- Hypersensitivity reactions [see Warnings and Precautions (5.1)].
- Hepatotoxicity [see Warnings and Precautions (5.2)].
- Immune Reconstitution Syndrome [see Warnings and Precautions (5.4)].

6.1 Clinical Trials Experience

Because clinical trials are conducted under widely varying conditions, adverse reaction rates observed in the clinical trials of a drug cannot be directly compared with rates in the clinical trials of another drug and may not reflect the rates observed in practice.

Clinical Trials Experience in Adult Subjects

Treatment-Naïve Subjects: The safety assessment of TIVICAY in HIV‑1–infected treatment-naïve subjects is based on the analyses of data from 2 international, multicenter, double-blind trials, SPRING-2 (ING113086) and SINGLE (ING114467) and data from the international, multicenter, open-label FLAMINGO (ING114915) trial.

In SPRING-2, 822 subjects were randomized and received at least 1 dose of either TIVICAY 50 mg once daily or raltegravir 400 mg twice daily, both in combination with fixed-dose dual nucleoside reverse transcriptase inhibitor (NRTI) treatment (either abacavir sulfate and lamivudine [EPZICOM] or emtricitabine/tenofovir [TRUVADA]). There were 808 subjects included in the efficacy and safety analyses. Through 96 weeks, the rate of adverse events leading to discontinuation was 2% in both treatment arms.

In SINGLE, 833 subjects were randomized and received at least 1 dose of either TIVICAY 50 mg with fixed-dose abacavir sulfate and lamivudine (EPZICOM) once daily or fixed-dose efavirenz/emtricitabine/tenofovir (ATRIPLA) once daily (study treatment was blinded through Week 96 and open-label from Week 96 through Week 144). Through 144 weeks, the rates of adverse events leading to discontinuation were 4% in subjects receiving TIVICAY 50 mg once daily + EPZICOM and 14% in subjects receiving ATRIPLA once daily.

Treatment‑emergent adverse reactions of moderate to severe intensity observed in at least 2% of subjects in either treatment arm in SPRING-2 and SINGLE trials are provided in Table 5. Side-by-side tabulation is to simplify presentation; direct comparisons across trials should not be made due to differing trial designs.

Table 5. Treatment-Emergent Adverse Reactions of at Least Moderate Intensity (Grades 2 to 4) and at Least 2% Frequency in Treatment-Naïve Subjects in SPRING-2 (Week 96 Analysis) and SINGLE Trials (Week 144 Analysis)
System Organ Class/; Preferred Term | SPRING-2 |  | SINGLE
System Organ Class/; Preferred Term | TIVICAY; 50 mg Once Daily + 2 NRTIs; (n = 403) | Raltegravir; 400 mg Twice Daily + 2 NRTIs; (n = 405) | TIVICAY; 50 mg + EPZICOM Once Daily; (n = 414) | ATRIPLA; Once Daily; (n = 419)
Psychiatric
Insomnia | <1% | <1% | 3% | 3%
Depression | <1% | <1% | 1% | 2%
Abnormal dreams | <1% | <1% | <1% | 2%
Nervous System
Dizziness | <1% | <1% | <1% | 5%
Headache | <1% | <1% | 2% | 2%
Gastrointestinal
Nausea | 1% | 1% | <1% | 3%
Diarrhea | <1% | <1% | <1% | 2%
Skin and Subcutaneous Tissue
Rasha | 0 | <1% | <1% | 6%
General Disorders
Fatigue | <1% | <1% | 2% | 2%
Ear and Labyrinth
Vertigo | 0 | <1% | 0 | 2%
NRTI = Nucleoside Reverse Transcriptase Inhibitor.
a Includes pooled terms: rash, rash generalized, rash macular, rash maculo-papular, rash pruritic, and drug eruption.

In addition, Grade 1 insomnia was reported by 1% and less than 1% of subjects receiving TIVICAY and raltegravir, respectively, in SPRING-2; whereas in SINGLE the rates were 7% and 4% for TIVICAY and ATRIPLA, respectively. These events were not treatment limiting.

In a multicenter, open-label trial (FLAMINGO), 243 subjects received TIVICAY 50 mg once daily versus 242 subjects who received darunavir 800 mg/ritonavir 100 mg once daily, both in combination with investigator-selected NRTI background regimen (either EPZICOM or TRUVADA). There were 484 subjects included in the efficacy and safety analyses. Through 96 weeks, the rates of adverse events leading to discontinuation were 3% in subjects receiving TIVICAY and 6% in subjects receiving darunavir/ritonavir. The adverse reactions observed in FLAMINGO were generally consistent with those seen in SPRING-2 and SINGLE.

Treatment-Experienced, Integrase Strand Transfer Inhibitor-Naïve Subjects: In an international, multicenter, double-blind trial (ING111762, SAILING), 719 HIV‑1–infected, antiretroviral treatment-experienced adults were randomized and received either TIVICAY 50 mg once daily or raltegravir 400 mg twice daily with investigator-selected background regimen consisting of up to 2 agents, including at least one fully active agent. At 48 weeks, the rates of adverse events leading to discontinuation were 3% in subjects receiving TIVICAY 50 mg once daily + background regimen and 4% in subjects receiving raltegravir 400 mg twice daily + background regimen.

The only treatment‑emergent adverse reaction of moderate to severe intensity with at least 2% frequency in either treatment group was diarrhea, 2% (6 of 354) in subjects receiving TIVICAY 50 mg once daily + background regimen and 1% (5 of 361) in subjects receiving raltegravir 400 mg twice daily + background regimen.

Treatment-Experienced, Integrase Strand Transfer Inhibitor-Experienced Subjects: In a multicenter, open-label, single‑arm trial (ING112574, VIKING-3), 183 HIV‑1–infected, antiretroviral treatment-experienced adults with virological failure and current or historical evidence of raltegravir and/or elvitegravir resistance received TIVICAY 50 mg twice daily with the current failing background regimen for 7 days and with optimized background therapy from Day 8. The rate of adverse events leading to discontinuation was 4% of subjects at Week 48.

Treatment‑emergent adverse reactions in VIKING-3 were generally similar compared with observations with the 50-mg once-daily dose in adult Phase III trials.

Virologically Suppressed Subjects: The adverse reactions observed for TIVICAY plus rilpivirine in the Week 48 analysis of pooled data from 2 identical, international, multicenter, open-label trials (SWORD-1 and SWORD-2) of 513 HIV-1–infected, virologically suppressed subjects switching from their current antiretroviral regimen to TIVICAY plus rilpivirine, were consistent with the adverse reaction profiles and severities for the individual components when administered with other antiretroviral agents. There were no adverse reactions (Grades 2 to 4) with an incidence of at least 2% in either treatment arm at Week 48. The safety profile during the additional follow-up period through Week 148 were consistent with Week 48. The rate of adverse events leading to discontinuation through Week 48 was 4% in subjects receiving TIVICAY plus rilpivirine once daily and less than 1% in subjects who remained on their current antiretroviral regimen. In the pooled analyses, the proportion of subjects receiving TIVICAY plus rilpivirine who discontinued treatment due to an adverse event through Week 148 was 8%.

Less Common Adverse Reactions Observed in Treatment-Naïve and Treatment-Experienced Trials: The following adverse reactions occurred in less than 2% of treatment-naïve or treatment-experienced subjects receiving TIVICAY in a combination regimen in any one trial. These events have been included because of their seriousness and assessment of potential causal relationship.

Gastrointestinal Disorders: Abdominal pain, abdominal discomfort, flatulence, upper abdominal pain, vomiting.

Hepatobiliary Disorders: Hepatitis.

Musculoskeletal Disorders: Myositis.

Psychiatric Disorders: Suicidal ideation, attempt, behavior, or completion. These events were observed primarily in subjects with a pre-existing history of depression or other psychiatric illness.

Renal and Urinary Disorders: Renal impairment.

Skin and Subcutaneous Tissue Disorders: Pruritus.

Laboratory Abnormalities:

Treatment-Naïve Subjects: Selected laboratory abnormalities (Grades 2 to 4) with a worsening grade from baseline and representing the worst-grade toxicity in at least 2% of subjects are presented in Table 6. The mean change from baseline observed for selected lipid values is presented in Table 7. Side-by-side tabulation is to simplify presentation; direct comparisons across trials should not be made due to differing trial designs.

Table 6. Selected Laboratory Abnormalities (Grades 2 to 4) in Treatment-Naïve Subjects in SPRING-2 (Week 96 Analysis) and SINGLE Trials (Week 144 Analysis)
Laboratory Parameter; Preferred Term | SPRING-2 |  | SINGLE
Laboratory Parameter; Preferred Term | TIVICAY 50 mg Once Daily + 2 NRTIs; (n = 403) | Raltegravir; 400 mg Twice Daily + 2 NRTIs; (n = 405) | TIVICAY 50 mg + EPZICOM Once Daily; (n = 414) | ATRIPLA; Once Daily; (n = 419)
ALT
Grade 2 (>2.5-5.0 x ULN) | 4% | 4% | 3% | 5%
Grade 3 to 4 (>5.0 x ULN) | 2% | 2% | 1% | <1%
AST
Grade 2 (>2.5-5.0 x ULN) | 5% | 3% | 3% | 4%
Grade 3 to 4 (>5.0 x ULN) | 3% | 2% | 1% | 3%
Total Bilirubin
Grade 2 (1.6-2.5 x ULN) | 3% | 2% | <1% | <1%
Grade 3 to 4 (>2.5 x ULN) | <1% | <1% | <1% | <1%
Creatine kinase
Grade 2 (6.0-9.9 x ULN) | 2% | 5% | 5% | 3%
Grade 3 to 4 (≥10.0 x ULN) | 7% | 4% | 7% | 8%
Hyperglycemia
Grade 2 (126 250 mg/dL) | 6% | 6% | 9% | 6%
Grade 3 (>250 mg/dL) | <1% | 2% | 2% | <1%
Lipase
Grade 2 (>1.5-3.0 x ULN) | 7% | 7% | 11% | 11%
Grade 3 to 4 (>3.0 x ULN) | 2% | 5% | 5% | 4%
Total neutrophils
Grade 2 (0.75-0.99 x 10^9) | 4% | 3% | 4% | 5%
Grade 3 to 4 (<0.75 x 10^9) | 2% | 2% | 3% | 3%
ALT = Alanine aminotransferase; AST = Aspartate aminotransferase; NRTI = Nucleoside Reverse Transcriptase Inhibitor; ULN = Upper limit of normal.

Table 7. Mean Change from Baseline in Fasted Lipid Values in Treatment-Naïve Subjects in SPRING-2 (Week 96 Analysisa) and SINGLE Trials (Week 144 Analysisa)
Laboratory Parameter; Preferred Term | SPRING-2 |  | SINGLE
Laboratory Parameter; Preferred Term | TIVICAY; 50 mg Once Daily + 2 NRTIs; (n = 403) | Raltegravir; 400 mg Twice Daily + 2 NRTIs; (n = 405) | TIVICAY; 50 mg + EPZICOM Once Daily; (n = 414) | ATRIPLA; Once Daily; (n = 419)
Cholesterol (mg/dL) | 8.1 | 10.1 | 24.0 | 26.7
HDL cholesterol (mg/dL) | 2.0 | 2.3 | 5.4 | 7.2
LDL cholesterol (mg/dL) | 5.1 | 6.1 | 16.0 | 14.6
Triglycerides (mg/dL) | 6.7 | 6.6 | 13.6 | 31.9
HDL = High density lipoprotein; LDL = Low density lipoprotein; NRTI = Nucleoside Reverse Transcriptase Inhibitor.
a Subjects on lipid-lowering agents at baseline were excluded from these analyses (19 subjects in each arm in SPRING-2, and in SINGLE: TIVICAY + EPZICOM n = 30 and ATRIPLA n = 27). Ninety-four subjects initiated a lipid-lowering agent post-baseline; their last fasted on-treatment values (prior to starting the agent) were used regardless of whether they discontinued the agent (SPRING-2: TIVICAY n = 9, raltegravir n = 13; SINGLE: TIVICAY + EPZICOM n = 36, ATRIPLA n = 36).

Laboratory abnormalities observed in the FLAMINGO trial were generally consistent with observations in SPRING-2 and SINGLE.

Treatment-Experienced, Integrase Strand Transfer Inhibitor-Naïve Subjects: Laboratory abnormalities observed in SAILING were generally similar compared with observations seen in the treatment-naïve (SPRING-2 and SINGLE) trials.

Treatment-Experienced, Integrase Strand Transfer Inhibitor-Experienced Subjects: The most common treatment-emergent laboratory abnormalities (greater than 5% for Grades 2 to 4 combined) observed in VIKING-3 at Week 48 were elevated ALT (9%), AST (8%), cholesterol (10%), creatine kinase (6%), hyperglycemia (14%), and lipase (10%). Two percent (4 of 183) of subjects had a Grade 3 to 4 treatment-emergent hematology laboratory abnormality, with neutropenia (2% [3 of 183]) being the most frequently reported.

Virologically Suppressed Adults: Laboratory abnormalities observed in SWORD-1 and SWORD-2 were generally similar compared with observations seen in the other Phase III trials.

Hepatitis B and/or Hepatitis C Virus Co-infection: In Phase III trials, subjects with hepatitis B and/or C virus co-infection were permitted to enroll provided that baseline liver chemistry tests did not exceed 5 times the upper limit of normal. Overall, the safety profile in subjects with hepatitis B and/or C virus co-infection was similar to that observed in subjects without hepatitis B or C co-infection, although the rates of AST and ALT abnormalities were higher in the subgroup with hepatitis B and/or C virus co-infection for all treatment groups. Grades 2 to 4 ALT abnormalities in hepatitis B and/or C co-infected compared with HIV mono-infected subjects receiving TIVICAY were observed in 18% vs. 3% with the 50-mg once-daily dose and 13% vs. 8% with the 50-mg twice-daily dose. Liver chemistry elevations consistent with immune reconstitution syndrome were observed in some subjects with hepatitis B and/or C at the start of therapy with TIVICAY, particularly in the setting where anti-hepatitis therapy was withdrawn [see Warnings and Precautions (5.2)].

Changes in Serum Creatinine: Dolutegravir has been shown to increase serum creatinine due to inhibition of tubular secretion of creatinine without affecting renal glomerular function [see Clinical Pharmacology (12.2)]. Increases in serum creatinine occurred within the first 4 weeks of treatment and remained stable through 96 weeks. In treatment-naïve subjects, a mean change from baseline of 0.15 mg/dL (range: -0.32 mg/dL to 0.65 mg/dL) was observed after 96 weeks of treatment. Creatinine increases were comparable by background NRTIs and were similar in treatment-experienced subjects.

Clinical Trials Experience in Pediatric Subjects

The safety and pharmacokinetics of TIVICAY and TIVICAY PD in HIV-1–infected pediatric subjects aged at least 4 weeks and weighing at least 3 kg was evaluated in the IMPAACT P1093 trial and 2 weight-band-based pharmacokinetic substudies of the ODYSSEY trial [see Use in Specific Populations (8.4), Clinical Pharmacology (12.3)]. Overall, the safety data in these pediatric studies were similar to those seen in adults, and there was no clinically significant difference in dolutegravir exposure [see Clinical Pharmacology (12.3)].

IMPAACT P1093 is an ongoing, multicenter, open-label, non-comparative trial of HIV‑1–infected pediatric subjects aged 4 weeks to less than 18 years [see Use in Specific Populations (8.4), Clinical Pharmacology (12.3), Clinical Studies (14.3)].

The safety analysis based on subjects (n = 75) who received the recommended dose (determined by weight and age) through Week 24 showed that 11% of subjects experienced drug-related clinical adverse reactions. The only Grade 1 to 2 drug-related clinical adverse reactions reported by more than one subject was immune reconstitution inflammatory syndrome (IRIS) (n = 2). There were no Grade 3 or 4 drug-related adverse reactions reported. No adverse reactions led to discontinuation.

The Grade 3 or 4 laboratory abnormalities reported in more than one subject were decreased neutrophil count (n = 11), decreased blood bicarbonate (n = 4), decreased hemoglobin (n = 3), increased lipase (n = 2), and increased blood potassium (n = 2). These laboratory events were not considered to be drug-related. Median laboratory values were similar at baseline and Week 24. Changes in median serum creatinine were similar to those observed in adults.

6.2 Postmarketing Experience

In addition to adverse reactions reported from clinical trials, the following adverse reactions have been identified during postmarketing use. Because these reactions are reported voluntarily from a population of uncertain size, it is not always possible to reliably estimate their frequency or establish a causal relationship to drug exposure.

Blood and Lymphatic Systems

Sideroblastic anemia.

Hepatobiliary Disorders

Acute liver failure, hepatotoxicity.

Investigations

Weight increased.

Musculoskeletal

Arthralgia, myalgia.

Psychiatric

Anxiety.

7 DRUG INTERACTIONS

7.1 Effect of Dolutegravir on the Pharmacokinetics of Other Agents

In vitro, dolutegravir inhibited the renal organic cation transporters, OCT2 (IC50 = 1.93 microM) and multidrug and toxin extrusion transporter (MATE) 1 (IC50 = 6.34 microM). In vivo, dolutegravir inhibits tubular secretion of creatinine by inhibiting OCT2 and potentially MATE1. Dolutegravir may increase plasma concentrations of drugs eliminated via OCT2 or MATE1 (dofetilide, dalfampridine, and metformin, Table 8) [see Contraindications (4), Drug Interactions (7.3)].

In vitro, dolutegravir inhibited the basolateral renal transporters, organic anion transporter (OAT) 1 (IC50 = 2.12 microM) and OAT3 (IC50 = 1.97 microM). However, in vivo, dolutegravir did not alter the plasma concentrations of tenofovir or para-amino hippurate, substrates of OAT1 and OAT3.

In vitro, dolutegravir did not inhibit (IC50 greater than 50 microM) the following: cytochrome P450 (CYP)1A2, CYP2A6, CYP2B6, CYP2C8, CYP2C9, CYP2C19, CYP2D6, CYP3A, uridine diphosphate glucuronosyltransferase (UGT)1A1, UGT2B7, P-glycoprotein (P-gp), breast cancer resistance protein (BCRP), bile salt export pump (BSEP), organic anion transporter polypeptide (OATP)1B1, OATP1B3, OCT1, multidrug resistance protein (MRP)2, or MRP4. In vitro, dolutegravir did not induce CYP1A2, CYP2B6, or CYP3A4. Based on these data and the results of drug interaction trials, dolutegravir is not expected to affect the pharmacokinetics of drugs that are substrates of these enzymes or transporters.

7.2 Effect of Other Agents on the Pharmacokinetics of Dolutegravir

Dolutegravir is metabolized by UGT1A1 with some contribution from CYP3A. Dolutegravir is also a substrate of UGT1A3, UGT1A9, BCRP, and P-gp in vitro. Drugs that induce those enzymes and transporters may decrease dolutegravir plasma concentration and reduce the therapeutic effect of dolutegravir.

Coadministration of dolutegravir and other drugs that inhibit these enzymes may increase dolutegravir plasma concentration.

Etravirine significantly reduced plasma concentrations of dolutegravir, but the effect of etravirine was mitigated by coadministration of lopinavir/ritonavir or darunavir/ritonavir and is expected to be mitigated by atazanavir/ritonavir (Table 8) [see Drug Interactions (7.3), Clinical Pharmacology (12.3)].

In vitro, dolutegravir was not a substrate of OATP1B1 or OATP1B3.

7.3 Established and Other Potentially Significant Drug Interactions

Table 8 provides clinical recommendations as a result of drug interactions with TIVICAY or TIVICAY PD. These recommendations are based on either drug interaction trials or predicted interactions due to the expected magnitude of interaction and potential for serious adverse events or loss of efficacy [see Dosage and Administration (2), Clinical Pharmacology (12.3)].

Table 8. Established and Other Potentially Significant Drug Interactions: Alterations in Dose or Regimen May Be Recommended Based on Drug Interaction Trials or Predicted Interactions [see Dosage and Administration (2)]
Concomitant Drug Class: Drug Name | Effect on Concentration of Dolutegravir and/or Concomitant Drug | Clinical Comment
HIV-1 Antiviral Agents
Non-nucleoside reverse transcriptase inhibitor:; Etravirinea | ↓Dolutegravir | Use of TIVICAY or TIVICAY PD with etravirine without coadministration of atazanavir/ritonavir, darunavir/ritonavir, or lopinavir/ritonavir is not recommended.
Non-nucleoside reverse transcriptase inhibitor:; Efavirenza | ↓Dolutegravir | Adjust dose of TIVICAY to twice daily for treatment-naïve and treatment-experienced, INSTI-naïve adult patients.; In pediatric patients, increase the weight-based dose of TIVICAY or TIVICAY PD to twice daily (Tables 2, 3, and 4).; Use alternative combinations that do not include metabolic inducers where possible for INSTI-experienced patients with certain INSTI-associated resistance substitutions or clinically suspected INSTI resistance.b
Non-nucleoside reverse transcriptase inhibitor:; Nevirapine | ↓Dolutegravir | Avoid coadministration with nevirapine because there are insufficient data to make dosing recommendations.
Protease inhibitors:; Fosamprenavir/ritonavira; Tipranavir/ritonavira | ↓Dolutegravir | Adjust dose of TIVICAY to twice daily for treatment-naïve and treatment-experienced, INSTI-naïve adult patients.; In pediatric patients, increase the weight-based dose of TIVICAY or TIVICAY PD to twice daily (Tables 2, 3, and 4).; Use alternative combinations that do not include metabolic inducers where possible for INSTI-experienced patients with certain INSTI-associated resistance substitutions or clinically suspected INSTI resistance.b
Other Agents
Dofetilide | ↑Dofetilide | Coadministration is contraindicated with TIVICAY or TIVICAY PD [see Contraindications (4)].
Carbamazepinea | ↓Dolutegravir | Adjust dose of TIVICAY to twice daily in treatment-naïve or treatment-experienced, INSTI-naïve adult patients.; In pediatric patients, increase the weight-based dose of TIVICAY or TIVICAY PD to twice daily (Tables 2, 3, and 4).; Use alternative treatment that does not include carbamazepine where possible for INSTI-experienced patients with certain INSTI-associated resistance substitutions or clinically suspected INSTI resistance.b
Oxcarbazepine Phenytoin Phenobarbital St. John’s wort (Hypericum perforatum) | ↓Dolutegravir | Avoid coadministration with TIVICAY or TIVICAY PD because there are insufficient data to make dosing recommendations.
Medications containing polyvalent cations (e.g., Mg or Al):; Cation-containing antacidsa or laxatives Sucralfate Buffered medications | ↓Dolutegravir | Administer TIVICAY or TIVICAY PD 2 hours before or 6 hours after taking medications containing polyvalent cations.
Oral calcium or iron supplements, including multivitamins containing calcium or irona | ↓Dolutegravir | When taken with food, TIVICAY and supplements or multivitamins containing calcium or iron can be taken at the same time. Under fasting conditions, TIVICAY or TIVICAY PD should be taken 2 hours before or 6 hours after taking supplements containing calcium or iron.
Potassium channel blocker:; Dalfampridine | ↑Dalfampridine | Elevated levels of dalfampridine increase the risk of seizures. The potential benefits of taking dalfampridine concurrently with TIVICAY or TIVICAY PD should be considered against the risk of seizures in these patients.
Metformin | ↑Metformin | Refer to the prescribing information for metformin for assessing the benefit and risk of concomitant use of TIVICAY or TIVICAY PD and metformin.
Rifampina | ↓Dolutegravir | Adjust dose of TIVICAY to twice daily for treatment-naïve and treatment-experienced, INSTI-naïve adult patients.; In pediatric patients, increase the weight-based dose of TIVICAY or TIVICAY PD to twice daily (Tables 2, 3, and 4).; Use alternatives to rifampin where possible for INSTI-experienced patients with certain INSTI-associated resistance substitutions or clinically suspected INSTI resistance.b
INSTI = integrase strand transfer inhibitor.
a See Clinical Pharmacology (12.3) Table 11 or Table 12 for magnitude of interaction.
b The lower dolutegravir exposures observed in INSTI-experienced patients (with certain INSTI-associated resistance substitutions or clinically suspected INSTI resistance [see Microbiology (12.4)]) upon coadministration with certain inducers may result in loss of therapeutic effect and development of resistance to TIVICAY or other coadministered antiretroviral agents.

7.4 Drugs without Clinically Significant Interactions with Dolutegravir

Based on drug interaction trial results, the following drugs can be coadministered with dolutegravir without a dose adjustment: atazanavir/ritonavir, darunavir/ritonavir, elbasvir/grazoprevir, methadone, midazolam, omeprazole, oral contraceptives containing norgestimate and ethinyl estradiol, prednisone, rifabutin, rilpivirine, sofosbuvir/velpatasvir, and tenofovir [see Clinical Pharmacology (12.3)].

8 USE IN SPECIFIC POPULATIONS

8.1 Pregnancy

Pregnancy Exposure Registry

There is a pregnancy exposure registry that monitors pregnancy outcomes in individuals exposed to TIVICAY or TIVICAY PD during pregnancy. Healthcare providers are encouraged to register patients by calling the Antiretroviral Pregnancy Registry (APR) at 1-800-258-4263.

Risk Summary

Data from two, ongoing birth outcome surveillance studies in Botswana and Eswatini which together include over 14,000 individuals evaluated during pregnancy show similar prevalence of neural tube defects among infants born to individuals taking dolutegravir at the time of conception compared to those born to individuals taking non-dolutegravir-containing regimens at conception or infants born to HIV-negative individuals. (see Data).

There are insufficient human data on the use of dolutegravir during pregnancy to definitively assess a drug-associated risk for birth defects and miscarriage. However, available human data from the APR do not indicate an increased risk of birth defects (see Data). The background risk for major birth defects for the indicated population is unknown. In the U.S. general population, the estimated background rate for major birth defects and miscarriage in clinically recognized pregnancies is 2% to 4% and 15% to 20%, respectively.

In animal reproduction studies, no evidence of adverse developmental outcomes (including neural tube defects) was observed with dolutegravir at systemic exposures (AUC) less than (rabbits) and approximately 27 times (rats) the exposure in humans at the maximum recommended human dose (MRHD) of TIVICAY (see Data).

Data

Human Data:

Observational studies: The first interim analysis from an ongoing birth outcome surveillance study in Botswana identified an association between dolutegravir and an increased risk of neural tube defects when dolutegravir was administered at the time of conception and in early pregnancy. A subsequent analysis was conducted based on a larger cohort from the birth outcome surveillance study in Botswana and included over 9,460 individuals exposed to dolutegravir at conception, 23,664 individuals exposed to non-dolutegravir-containing regimens, and 170,723 HIV-negative pregnant individuals. The prevalence of neural tube defects in infants delivered to individuals taking dolutegravir at conception was 0.11% (95% CI: 0.05-0.19%). The observed prevalence rate did not differ significantly from that of infants delivered to individuals taking non-dolutegravir-containing regimens (0.11%, 95% CI: 0.07-0.16%), or to HIV-negative individuals (0.06%, 95% CI: 0.05-0.08%).

The Eswatini birth outcome surveillance study includes 9,743 individuals exposed to dolutegravir at conception, 1,838 individuals exposed to non-dolutegravir-containing regimens, and 32,259 HIV-negative pregnant individuals. The prevalence of neural tube defects in infants delivered to individuals taking dolutegravir at conception was 0.08% (95% CI: 0.04-0.16%). The observed prevalence rate did not differ significantly from that of infants delivered to individuals taking non-dolutegravir-containing regimens (0.22%, 95% CI: 0.06-0.56%) or to HIV-negative individuals (0.08%, 95% CI: 0.06-0.12%). The observed prevalence of neural tube defects in infants delivered to individuals taking non-dolutegravir-containing regimens had a wide confidence interval due to low sample size.

Limitations of these birth outcome surveillance studies include insufficient data to determine if baseline characteristics were balanced between the study groups or to assess other factors such as the use of folic acid during the preconception or first trimester periods.

Antiretroviral Pregnancy Registry: Based on prospective reports to the APR, of 1,377 exposures to dolutegravir during pregnancy resulting in live births (including 874 exposed in the first trimester), the prevalence of defects in live births was 3.3% (95% CI: 2.2% to 4.7%) following first-trimester exposure to dolutegravir-containing regimens and 5.0% (95% CI: 3.2% to 7.3%) following second-/third-trimester exposure to dolutegravir-containing regimens. In the U.S. reference population of the Metropolitan Atlanta Congenital Defects Program (MACDP), the background birth defect rate was 2.7%.

Dolutegravir has been shown to cross the placenta. In a clinical trial in Uganda and South Africa in women during the last trimester of pregnancy receiving dolutegravir 50 mg once daily, the ratio of median dolutegravir concentration in fetal umbilical cord to that in maternal peripheral plasma was 1.21 (range 0.51 to 2.11) (n = 15).

Animal Data:

Dolutegravir was administered orally at up to 1,000 mg/kg daily to pregnant rats and rabbits on Gestation Days 6 to 17 and 6 to 18, respectively, and to rats on Gestation Day 6 to Lactation/Postpartum Day 20. No adverse effects on embryo-fetal (rats and rabbits) or pre/postnatal (rats) development were observed at up to the highest dose tested. During organogenesis, systemic exposures (AUC) to dolutegravir in rabbits were less than the exposure in humans at the MRHD and in rats were approximately 27 times the exposure in humans at the MRHD. In the rat pre/postnatal development study, decreased body weight of the developing offspring was observed during lactation at a maternally toxic dose (approximately 27 times human exposure at the MRHD).

8.2 Lactation

Risk Summary

Dolutegravir is present in human milk. It is not known whether dolutegravir affects human milk production or has effects on the breastfed infant.

Potential risks of breastfeeding include: (1) HIV‑1 transmission (in HIV-1–negative infants), (2) developing viral resistance (in HIV-1–positive infants), and (3) adverse reactions in a breastfed infant similar to those seen in adults.

8.4 Pediatric Use

The safety, pharmacokinetics, and effectiveness of TIVICAY and TIVICAY PD were evaluated in 75 HIV-1–infected, treatment-naïve or treatment-experienced, INSTI-naïve pediatric and adolescent subjects aged 4 weeks to less than 18 years weighing at least 3 kg in an ongoing, open-label, multicenter, dose-finding clinical trial, IMPAACT P1093 [see Adverse Reactions (6.1), Clinical Pharmacology (12.3), Clinical Studies (14.3)]. Additional pharmacokinetics data were evaluated in 2 pharmacokinetic substudies in ODYSSEY, an ongoing open-label, randomized, non-inferiority trial to evaluate the safety, efficacy, and pharmacokinetic parameters of TIVICAY or TIVICAY PD plus two NRTIs compared with standard of care in HIV-1–infected pediatric subjects younger than 18 years [see Clinical Pharmacology (12.3)].

Overall, the safety data in pediatric subjects from the IMPAACT P1093 trial were comparable to those observed in adults [see Adverse Reactions (6.1)]. The pharmacokinetic parameters of TIVICAY or TIVICAY PD in pediatric subjects from IMPAACT P1093 and ODYSSEY were comparable to those of adults receiving 50 mg once daily or twice daily [see Clinical Pharmacology (12.3)]. The effectiveness observed in IMPAACT P1093 is comparable to that of treatment-experienced adult subjects.

Safety and effectiveness of TIVICAY or TIVICAY PD have not been established in pediatric patients aged less than 4 weeks or weighing less than 3 kg or in any pediatric patients who are INSTI-experienced with documented or clinically suspected resistance to other INSTIs (e.g., raltegravir, elvitegravir).

8.5 Geriatric Use

Clinical trials of TIVICAY did not include sufficient numbers of subjects aged 65 and older to determine whether they respond differently from younger subjects. In general, caution should be exercised in the administration of TIVICAY in elderly patients reflecting the greater frequency of decreased hepatic, renal, or cardiac function, and of concomitant disease or other drug therapy [see Clinical Pharmacology (12.3)].

8.6 Hepatic Impairment

No clinically important pharmacokinetic differences between subjects with moderate hepatic impairment and matching healthy subjects were observed. No dosage adjustment is necessary for patients with mild to moderate hepatic impairment (Child-Pugh Score A or B). The effect of severe hepatic impairment (Child-Pugh Score C) on the pharmacokinetics of dolutegravir has not been studied. Therefore, TIVICAY and TIVICAY PD are not recommended for use in patients with severe hepatic impairment [see Clinical Pharmacology (12.3)].

8.7 Renal Impairment

Dolutegravir plasma concentrations were decreased in subjects with severe renal impairment compared with those in matched healthy controls. However, no dosage adjustment is necessary for treatment-naïve or treatment-experienced and INSTI-naïve patients with mild, moderate, or severe renal impairment or for INSTI-experienced patients (with certain INSTI-associated resistance substitutions or clinically suspected INSTI resistance) with mild or moderate renal impairment. Caution is warranted for INSTI-experienced patients (with certain INSTI-associated resistance substitutions or clinically suspected INSTI resistance [see Microbiology (12.4)]) with severe renal impairment, as the decrease in dolutegravir concentrations may result in loss of therapeutic effect and development of resistance to TIVICAY, TIVICAY PD, or other coadministered antiretroviral agents [see Clinical Pharmacology (12.3)]. There is inadequate information to recommend appropriate dosing of dolutegravir in patients requiring dialysis.

10 OVERDOSAGE

There is no known specific treatment for overdose with TIVICAY or TIVICAY PD. If overdose occurs, the patient should be monitored, and standard supportive treatment applied as required. As dolutegravir is highly bound to plasma proteins, it is unlikely that it will be significantly removed by dialysis.

11 DESCRIPTION

TIVICAY contains dolutegravir, as dolutegravir sodium, an HIV INSTI. The chemical name of dolutegravir sodium is sodium (4R,12aS)-9-{[(2,4-difluorophenyl)methyl]carbamoyl}-4-methyl-6,8-dioxo-3,4,6,8,12,12a-hexahydro-2H-pyrido[1',2':4,5]pyrazino[2,1-b][1,3]oxazin-7-olate. The empirical formula is C20H18F2N3NaO5, and the molecular weight is 441.36 g/mol. It has the following structural formula:

Dolutegravir sodium is a white to light yellow powder and is slightly soluble in water.

Each film-coated tablet of TIVICAY for oral administration contains 10.5, 26.3, or 52.6 mg of dolutegravir sodium, which is equivalent to 10, 25, or 50 mg dolutegravir free acid, respectively, and the following inactive ingredients: D-mannitol, microcrystalline cellulose, povidone K29/32, sodium starch glycolate, and sodium stearyl fumarate. The tablet film‑coating contains the inactive ingredients iron oxide yellow (25-mg and 50-mg tablets only), macrogol/PEG, polyvinyl alcohol-part hydrolyzed, talc, and titanium dioxide.

Each TIVICAY PD tablet for oral suspension contains 5.26 mg of dolutegravir sodium, which is equivalent to 5 mg dolutegravir free acid, and the following inactive ingredients: calcium sulfate dihydrate, crospovidone, mannitol, microcrystalline cellulose, povidone K29/32, silicified microcrystalline cellulose, sodium starch glycolate, strawberry cream flavor, sucralose, and sodium stearyl fumarate. The tablet film-coating contains hypromellose, polyethylene glycol, and titanium dioxide.

12 CLINICAL PHARMACOLOGY

12.1 Mechanism of Action

Dolutegravir is an HIV-1 antiretroviral agent [see Microbiology (12.4)].

12.2 Pharmacodynamics

Effects on Electrocardiogram

In a randomized, placebo-controlled, cross-over trial, 42 healthy subjects received single-dose oral administrations of placebo, dolutegravir 250-mg suspension (exposures approximately 3–fold of the 50-mg once-daily dose at steady state), and moxifloxacin 400 mg (active control) in random sequence. After baseline and placebo adjustment, the maximum mean QTc change based on Fridericia correction method (QTcF) for dolutegravir was 2.4 msec (1-sided 95% upper CI: 4.9 msec). TIVICAY did not prolong the QTc interval over 24 hours postdose.

Effects on Renal Function

The effect of dolutegravir on renal function was evaluated in an open-label, randomized, 3‑arm, parallel, placebo-controlled trial in healthy subjects (n = 37) who received dolutegravir 50 mg once daily (n = 12), dolutegravir 50 mg twice daily (n = 13), or placebo once daily (n = 12) for 14 days. A decrease in creatinine clearance, as determined by 24-hour urine collection, was observed with both doses of dolutegravir after 14 days of treatment in subjects who received 50 mg once daily (9% decrease) and 50 mg twice daily (13% decrease). Neither dose of dolutegravir had a significant effect on the actual glomerular filtration rate (determined by the clearance of probe drug, iohexol) or effective renal plasma flow (determined by the clearance of probe drug, para-amino hippurate) compared with the placebo.

12.3 Pharmacokinetics

The pharmacokinetic properties of dolutegravir have been evaluated in healthy adult subjects and HIV‑1–infected adult subjects. Exposure to dolutegravir was generally similar between healthy subjects and HIV‑1–infected subjects. The non-linear exposure of dolutegravir following 50 mg twice daily compared with 50 mg once daily in HIV‑1–infected subjects (Table 9) was attributed to the use of metabolic inducers in the background antiretroviral regimens of subjects receiving dolutegravir 50 mg twice daily in clinical trials.

Table 9. Dolutegravir Steady-State Pharmacokinetic Parameter Estimates in HIV-1–Infected Adults
Parameter | 50 mg Once Daily; Geometric Meana (%CV) | 50 mg Twice Daily; Geometric Meanb (%CV)
AUC(0-24) (mcg∙ h/mL) | 53.6 (27) | 75.1 (35)
Cmax (mcg/mL) | 3.67 (20) | 4.15 (29)
Cmin (mcg/mL) | 1.11 (46) | 2.12 (47)
a Based on population pharmacokinetic analyses using data from SPRING-1 and SPRING-2.
b Based on population pharmacokinetic analyses using data from VIKING (ING112961) and VIKING-3.

TIVICAY tablets and TIVICAY PD tablets for oral suspension are not bioequivalent. The relative bioavailability of TIVICAY PD is approximately 1.6-fold higher than TIVICAY; therefore, the 2 dosage forms are not substitutable on a milligram-per-milligram basis [see Dosage and Administration (2.3)].

Absorption

Following oral administration of dolutegravir, peak plasma concentrations were observed 1 to 3 hours postdose. With once-daily dosing, pharmacokinetic steady state is achieved within approximately 5 days with average accumulation ratios for AUC, Cmax, and C24 h ranging from 1.2 to 1.5.

Dolutegravir plasma concentrations increased in a less than dose-proportional manner above 50 mg. Dolutegravir is a P‑gp substrate in vitro. The absolute bioavailability of dolutegravir has not been established.

Effect of Food: TIVICAY or TIVICAY PD may be taken with or without food. Food increased the extent of absorption and slowed the rate of absorption of dolutegravir following a 50-mg dose of TIVICAY. Low-, moderate-, and high-fat meals increased dolutegravir AUC(0-∞) by 33%, 41%, and 66%; increased Cmax by 46%, 52%, and 67%; and prolonged Tmax to 3, 4, and 5 hours from 2 hours under fasted conditions, respectively.

Distribution

Dolutegravir is highly bound (greater than or equal to 98.9%) to human plasma proteins based on in vivo data and binding is independent of plasma concentration of dolutegravir. The apparent volume of distribution (Vd/F) following 50-mg once-daily administration is estimated at 17.4 L based on a population pharmacokinetic analysis.

Cerebrospinal Fluid (CSF): In 12 treatment-naïve subjects on dolutegravir 50 mg daily plus abacavir/lamivudine, the median dolutegravir concentration in CSF was 13.2 ng/mL (range: 3.74 ng/mL to 18.3 ng/mL) 2 to 6 hours postdose after 16 weeks of treatment. The clinical relevance of this finding has not been established.

Elimination

Dolutegravir has a terminal half-life of approximately 14 hours and an apparent clearance (CL/F) of 1.0 L/h based on population pharmacokinetic analyses.

Metabolism: Dolutegravir is primarily metabolized via UGT1A1 with some contribution from CYP3A.

Polymorphisms in Drug‑Metabolizing Enzymes: In a meta-analysis of healthy subject trials, subjects with UGT1A1 (n = 7) genotypes conferring poor dolutegravir metabolism had a 32% lower clearance of dolutegravir and 46% higher AUC compared with subjects with genotypes associated with normal metabolism via UGT1A1 (n = 41).

Excretion: After a single oral dose of [^14C] dolutegravir, 53% of the total oral dose was excreted unchanged in feces. Thirty-one percent of the total oral dose was excreted in urine, represented by an ether glucuronide of dolutegravir (18.9% of total dose), a metabolite formed by oxidation at the benzylic carbon (3.0% of total dose), and its hydrolytic N-dealkylation product (3.6% of total dose). Renal elimination of unchanged drug was low (less than 1% of the dose).

Specific Populations

Pediatric Patients: The pharmacokinetics of dolutegravir were evaluated in the IMPAACT P1093 trial and in 2 weight-band-based pharmacokinetic substudies from the ODYSSEY trial. Steady-state plasma exposure at doses by weight band are summarized in Table 10 [see Clinical Studies (14.3)].

Mean dolutegravir AUC0-24h and C24h in HIV-1–infected pediatric subjects were comparable to those in adults after 50 mg once daily or 50 mg twice daily. Mean Cmax is higher in pediatrics, but the increase is not considered clinically significant as the safety profiles were similar in pediatric and adult subjects [see Use in Specific Populations (8.4)].

Table 10. Summary of Pharmacokinetic Parameters in Pediatric HIV-1–Infected Subjects (Pooled Analyses for IMPAACT P1093 and ODYSSEYa Trials)
Weight Band | Doseb of TIVICAY or TIVICAY PD | n | Pharmacokinetic Parameter Geometric Mean (%CV)
Weight Band | Doseb of TIVICAY or TIVICAY PD | n | Cmax (mcg/mL) | AUC0-24h (mcg∙h/mL) | C24h (ng/mL)
3 kg to <6 kg | TIVICAY PD 5 mg once daily | 8 | 3.80 (34) | 49.37 (49) | 962 (98)
6 kg to <10 kg | TIVICAY PD 15 mg once daily | 17 | 5.27 (50) | 57.17 (76) | 706 (177)
10 kg to <14 kg | TIVICAY PD 20 mg once daily | 13 | 5.99 (33) | 68.75 (48) | 977 (100)
14 kg to <20 kg | TIVICAY PD 25 mg once daily | 19 | 5.97 (42) | 58.97 (44) | 725 (75)
20 kg to <25 kg | TIVICAY PD 30 mg once daily | 9 | 7.16 (26) | 71.53 (26) | 759 (73)
≥20 kg | TIVICAY 50 mg once daily | 49 | 4.92 (40) | 54.98 (43) | 778 (62)
a Data from 2 weight-band-based pharmacokinetic substudies in the ODYSSEY trial.
b The bioavailability of TIVICAY PD tablets for oral suspension is ~1.6-fold that of TIVICAY tablets.

Geriatric Patients: Population pharmacokinetic analysis indicated age had no clinically relevant effect on the pharmacokinetics of dolutegravir.

Patients with Hepatic Impairment: In a trial comparing 8 subjects with moderate hepatic impairment (Child-Pugh Score B) with 8 matched healthy controls, exposure of dolutegravir from a single 50-mg dose was similar between the 2 groups. The effect of severe hepatic impairment (Child-Pugh Score C) on the pharmacokinetics of dolutegravir has not been studied.

Patients with Renal Impairment: In a trial evaluating the pharmacokinetics of a single 50-mg tablet of dolutegravir comparing 8 subjects with severe renal impairment (CrCl less than 30 mL/min) with 8 matched healthy controls, AUC, Cmax, and C24 of dolutegravir were lower by 40%, 23%, and 43%, respectively, compared with those in matched healthy subjects. Population pharmacokinetic analysis using data from SAILING and VIKING-3 trials indicated that mild and moderate renal impairment had no clinically relevant effect on the exposure of dolutegravir. There is inadequate information to recommend appropriate dosing of dolutegravir in patients requiring dialysis.

HBV or HCV Co-infected Patients: Population analyses using pooled pharmacokinetic data from adult trials indicated no clinically relevant effect of HCV co-infection on the pharmacokinetics of dolutegravir. There were limited data on HBV co-infection.

Gender and Race: Population analyses using pooled pharmacokinetic data from adult trials indicated gender and race had no clinically relevant effect on the exposure of dolutegravir.

Drug Interaction Studies

Drug interaction trials were performed with TIVICAY and other drugs likely to be coadministered or commonly used as probes for pharmacokinetic interactions. The effects of dolutegravir on the exposure of coadministered drugs are summarized in Table 11 and the effects of coadministered drugs on the exposure of dolutegravir are summarized in Table 12.

Dosing or regimen recommendations as a result of established and other potentially significant drug-drug interactions with TIVICAY are provided in Table 8 [see Dosage and Administration (2.2), Drug Interactions (7.3)].

Table 11. Summary of Effect of Dolutegravir on the Pharmacokinetics of Coadministered Drugs
Coadministered Drug(s); and Dose(s) | Dose of TIVICAY | n | Geometric Mean Ratio (90% CI) of Pharmacokinetic Parameters of Coadministered Drug with/without Dolutegravir No Effect = 1.00
Coadministered Drug(s); and Dose(s) | Dose of TIVICAY | n | Cmax | AUC | Cτ or C24
Elbasvir; 50 mg once daily | 50 mg; single dose | 12 | 0.97; (0.89, 1.05) | 0.98; (0.93, 1.04) | 0.98; (0.93, 1.03)
Ethinyl estradiol 0.035 mg | 50 mg twice daily | 15 | 0.99 (0.91 to 1.08) | 1.03 (0.96 to 1.11) | 1.02 (0.93 to 1.11)
Grazoprevir; 200 mg once daily | 50 mg; single dose | 12 | 0.64; (0.44, 0.93) | 0.81; (0.67, 0.97) | 0.86; (0.79, 0.93)
Metformin 500 mg twice daily | 50 mg once daily | 15a | 1.66 (1.53 to 1.81) | 1.79 (1.65 to 1.93) | _
Metformin 500 mg twice daily | 50 mg twice daily | 15a | 2.11 (1.91 to 2.33) | 2.45 (2.25 to 2.66) | _
Methadone 16 to 150 mg | 50 mg twice daily | 11 | 1.00 (0.94 to 1.06) | 0.98 (0.91 to 1.06) | 0.99 (0.91 to 1.07)
Midazolam 3 mg | 25 mg once daily | 10 | _ | 0.95 (0.79 to 1.15) | _
Norelgestromin 0.25 mg | 50 mg twice daily | 15 | 0.89 (0.82 to 0.97) | 0.98 (0.91 to 1.04) | 0.93 (0.85 to 1.03)
Rilpivirine 25 mg once daily | 50 mg once daily | 16 | 1.10 (0.99 to 1.22) | 1.06 (0.98 to 1.16) | 1.21 (1.07 to 1.38)
Sofosbuvir; 400 mg once daily; Metabolite (GS-331007) | 50 mg; once daily | 24 | 0.88; (0.80, 0.98) | 0.92; (0.85, 0.99) | NA
Sofosbuvir; 400 mg once daily; Metabolite (GS-331007) | 50 mg; once daily | 24 | 1.01; (0.93, 1.10) | 0.99; (0.97, 1.01) | 0.99; (0.97, 1.01)
Tenofovir disoproxil fumarate 300 mg once daily | 50 mg once daily | 15 | 1.09 (0.97 to 1.23) | 1.12 (1.01 to 1.24) | 1.19 (1.04 to 1.35)
Velpatasvir; 100 mg once daily | 50 mg; once daily | 24 | 0.94; (0.86, 1.02) | 0.91; (0.84, 0.98) | 0.88; (0.82, 0.94)
a The number of subjects represents the maximum number of subjects that were evaluated.

Table 12. Summary of Effect of Coadministered Drugs on the Pharmacokinetics of Dolutegravir
Coadministered Drug(s); and Dose(s) | Dose of TIVICAY | n | Geometric Mean Ratio (90% CI) of Dolutegravir Pharmacokinetic Parameters with/without Coadministered Drugs No Effect = 1.00
Coadministered Drug(s); and Dose(s) | Dose of TIVICAY | n | Cmax | AUC | Cτ or C24
Atazanavir 400 mg once daily | 30 mg once daily | 12 | 1.50 (1.40 to 1.59) | 1.91 (1.80 to 2.03) | 2.80 (2.52 to 3.11)
Atazanavir/ritonavir 300/100 mg once daily | 30 mg once daily | 12 | 1.34 (1.25 to 1.42) | 1.62 (1.50 to 1.74) | 2.21 (1.97 to 2.47)
Darunavir/ritonavir 600/100 mg twice daily | 30 mg once daily | 15 | 0.89 (0.83 to 0.97) | 0.78 (0.72 to 0.85) | 0.62 (0.56 to 0.69)
Efavirenz 600 mg once daily | 50 mg once daily | 12 | 0.61 (0.51 to 0.73) | 0.43 (0.35 to 0.54) | 0.25 (0.18 to 0.34)
Elbasvir/grazoprevir; 50/200 mg once daily | 50 mg; single dose | 12 | 1.22; (1.05, 1.40) | 1.16; (1.00, 1.34) | 1.14; (0.95, 1.36)
Etravirine 200 mg twice daily | 50 mg once daily | 16 | 0.48 (0.43 to 0.54) | 0.29 (0.26 to 0.34) | 0.12 (0.09 to 0.16)
Etravirine + darunavir/ritonavir 200 mg + 600/100 mg twice daily | 50 mg once daily | 9 | 0.88 (0.78 to 1.00) | 0.75 (0.69 to 0.81) | 0.63 (0.52 to 0.76)
Etravirine + lopinavir/ritonavir 200 mg + 400/100 mg twice daily | 50 mg once daily | 8 | 1.07 (1.02 to 1.13) | 1.11 (1.02 to 1.20) | 1.28 (1.13 to 1.45)
Fosamprenavir/ritonavir 700 mg/100 mg twice daily | 50 mg once daily | 12 | 0.76 (0.63 to 0.92) | 0.65 (0.54 to 0.78) | 0.51 (0.41 to 0.63)
Lopinavir/ritonavir 400/100 mg twice daily | 30 mg once daily | 15 | 1.00 (0.94 to 1.07) | 0.97 (0.91 to 1.04) | 0.94 (0.85 to 1.05)
Rilpivirine 25 mg once daily | 50 mg once daily | 16 | 1.13 (1.06 to 1.21) | 1.12 (1.05 to 1.19) | 1.22 (1.15 to 1.30)
Tenofovir 300 mg once daily | 50 mg once daily | 15 | 0.97 (0.87 to 1.08) | 1.01 (0.91 to 1.11) | 0.92; (0.82 to 1.04)
Tipranavir/ritonavir 500/200 mg twice daily | 50 mg once daily | 14 | 0.54 (0.50 to 0.57) | 0.41 (0.38 to 0.44) | 0.24 (0.21 to 0.27)
Antacid (MAALOX) simultaneous administration | 50 mg single dose | 16 | 0.28 (0.23 to 0.33) | 0.26 (0.22 to 0.32) | 0.26 (0.21 to 0.31)
Antacid (MAALOX) 2 h after dolutegravir | 50 mg single dose | 16 | 0.82 (0.69 to 0.98) | 0.74 (0.62 to 0.90) | 0.70 (0.58 to 0.85)
Calcium carbonate 1,200 mg simultaneous administration (fasted) | 50 mg single dose | 12 | 0.63 (0.50 to 0.81) | 0.61 (0.47 to 0.80) | 0.61 (0.47 to 0.80)
Calcium carbonate 1,200 mg simultaneous administration (fed) | 50 mg single dose | 11 | 1.07 (0.83 to 1.38) | 1.09 (0.84 to 1.43) | 1.08 (0.81 to 1.42)
Calcium carbonate 1,200 mg 2 h after dolutegravir | 50 mg single dose | 11 | 1.00 (0.78 to 1.29) | 0.94 (0.72 to 1.23) | 0.90 (0.68 to 1.19)
Carbamazepine 300 mg twice daily | 50 mg once daily | 16a | 0.67 (0.61 to 0.73) | 0.51 (0.48 to 0.55) | 0.27 (0.24 to 0.31)
Ferrous fumarate 324 mg simultaneous administration (fasted) | 50 mg single dose | 11 | 0.43 (0.35 to 0.52) | 0.46 (0.38 to 0.56) | 0.44 (0.36 to 0.54)
Ferrous fumarate 324 mg simultaneous administration (fed) | 50 mg single dose | 11 | 1.03 (0.84 to 1.26) | 0.98 (0.81 to 1.20) | 1.00 (0.81 to 1.23)
Ferrous fumarate 324 mg 2 h after dolutegravir | 50 mg single dose | 10 | 0.99 (0.81 to 1.21) | 0.95 (0.77 to 1.15) | 0.92 (0.74 to 1.13)
Multivitamin (One-A-Day) simultaneous administration | 50 mg single dose | 16 | 0.65 (0.54 to 0.77) | 0.67 (0.55 to 0.81) | 0.68 (0.56 to 0.82)
Omeprazole 40 mg once daily | 50 mg single dose | 12 | 0.92 (0.75 to 1.11) | 0.97 (0.78 to 1.20) | 0.95 (0.75 to 1.21)
Prednisone 60 mg once daily with taper | 50 mg once daily | 12 | 1.06 (0.99 to 1.14) | 1.11 (1.03 to 1.20) | 1.17 (1.06 to 1.28)
Rifampinb 600 mg once daily | 50 mg twice daily | 11 | 0.57 (0.49 to 0.65) | 0.46 (0.38 to 0.55) | 0.28 (0.23 to 0.34)
Rifampinc 600 mg once daily | 50 mg twice daily | 11 | 1.18 (1.03 to 1.37) | 1.33 (1.15 to 1.53) | 1.22 (1.01 to 1.48)
Rifabutin 300 mg once daily | 50 mg once daily | 9 | 1.16 (0.98 to 1.37) | 0.95 (0.82 to 1.10) | 0.70 (0.57 to 0.87)
a The number of subjects represents the maximum number of subjects that were evaluated.
b Comparison is rifampin taken with dolutegravir 50 mg twice daily compared with dolutegravir 50 mg twice daily.
c Comparison is rifampin taken with dolutegravir 50 mg twice daily compared with dolutegravir 50 mg once daily.

12.4 Microbiology

Mechanism of Action

Dolutegravir inhibits HIV integrase by binding to the integrase active site and blocking the strand transfer step of retroviral DNA integration which is essential for the HIV replication cycle. Strand transfer biochemical assays using purified HIV-1 integrase and pre-processed substrate DNA resulted in IC50 values of 2.7 nM and 12.6 nM.

Antiviral Activity in Cell Culture

Dolutegravir exhibited antiviral activity against laboratory strains of wild-type HIV-1 with mean EC50 values of 0.5 nM (0.21 ng/mL) to 2.1 nM (0.85 ng/mL) in peripheral blood mononuclear cells (PBMCs) and MT-4 cells. Dolutegravir exhibited antiviral activity against 13 clinically diverse clade B isolates with a mean EC50 value of 0.52 nM in a viral integrase susceptibility assay using the integrase coding region from clinical isolates. Dolutegravir demonstrated antiviral activity in cell culture against a panel of HIV-1 clinical isolates (3 in each group of M clades A, B, C, D, E, F, and G, and 3 in group O) with EC50 values ranging from 0.02 nM to 2.14 nM for HIV-1. Dolutegravir EC50 values against 3 HIV-2 clinical isolates in PBMC assays ranged from 0.09 nM to 0.61 nM.

Antiviral Activity in Combination with Other Antiviral Agents

The antiviral activity of dolutegravir was not antagonistic when combined with the INSTI, raltegravir; non-nucleoside reverse transcriptase inhibitors (NNRTIs), efavirenz or nevirapine; the NRTIs, abacavir or stavudine; the protease inhibitors (PIs), amprenavir or lopinavir; the CCR5 co-receptor antagonist, maraviroc; or the fusion inhibitor, enfuvirtide. Dolutegravir antiviral activity was not antagonistic when combined with the HBV reverse transcriptase inhibitor, adefovir, or inhibited by the antiviral, ribavirin.

Resistance

Cell Culture: Dolutegravir-resistant viruses were selected in cell culture starting from different wild-type HIV-1 strains and clades. Amino acid substitutions E92Q, G118R, S153F or Y, G193E or R263K emerged in different passages and conferred decreased susceptibility to dolutegravir of up to 4-fold. Passage of mutant viruses containing the Q148R or Q148H substitutions selected for additional substitutions in integrase that conferred decreased susceptibility to dolutegravir (fold-change increase of 13 to 46). The additional integrase substitutions included T97A, E138K, G140S, and M154I. Passage of mutant viruses containing both G140S and Q148H selected for L74M, E92Q, and N155H.

Treatment-Naïve Subjects: No subject who received dolutegravir 50-mg once-daily in the treatment-naïve trials SPRING-2 (96 weeks) and SINGLE (144 weeks) had a detectable decrease in susceptibility to dolutegravir or background NRTIs in the resistance analysis subset (n = 12 with HIV-1 RNA greater than 400 copies per mL at failure or last visit and having resistance data). Two virologic failure subjects in SINGLE had treatment-emergent G/D/E193D and G193G/E integrase substitutions at Week 84 and Week 108, respectively, and 1 subject with 275 copies/mLHIV-1 RNA had a treatment-emergent Q157Q/P integrase substitution detected at Week 24. None of these subjects had a corresponding decrease in dolutegravir susceptibility. No treatment-emergent genotypic resistance to the background regimen was observed in the dolutegravir arm in either the SPRING-2 or SINGLE trials. No treatment-emergent primary resistance substitutions were observed in either treatment group in the FLAMINGO trial through Week 96.

Treatment-Experienced, Integrase Strand Transfer Inhibitor-Naïve Subjects: In the dolutegravir arm of the SAILING trial for treatment-experienced and INSTI-naïve subjects (n = 354), treatment-emergent integrase substitutions were observed in 6 of 28 (21%) subjects who had virologic failure and resistance data. In 5 of the 6 subjects’ isolates emergent INSTI substitutions included L74L/M/I, Q95Q/L, V151V/I (n = 1 each), and R263K (n = 2). The change in dolutegravir phenotypic susceptibility for these 5 subject isolates was less than 2-fold. One subject isolate had pre-existing raltegravir resistance substitutions E138A, G140S, and Q148H at baseline and had additional emergent INSTI-resistance substitutions T97A and E138A/T with a corresponding 148-fold reduction in dolutegravir susceptibility at failure. In the comparator raltegravir arm, 21 of 49 (43%) subjects with post-baseline resistance data had evidence of emergent INSTI-resistance substitutions (L74M, E92Q, T97A, E138Q, G140S/A, Y143R/C, Q148H/R, V151I, N155H, E157Q, and G163K/R) and raltegravir phenotypic resistance.

Virologically Suppressed Subjects: SWORD-1 and SWORD-2 are identical trials in virologically suppressed subjects receiving 2 NRTIs plus either an INSTI, an NNRTI, or a PI, that switched to dolutegravir plus rilpivirine (n = 513) or remained on their current antiviral regimen (n = 511). In the pooled SWORD-1 and SWORD-2 trials, 12 subjects (7 in SWORD-1 and 5 in SWORD-2) had confirmed virologic failure (HIV-1 RNA greater than 200 copies/mL) while receiving dolutegravir plus rilpivirine at any time through Week 148. Ten of the confirmed virologic failures had post-baseline resistance data, with 6 isolates showing evidence of rilpivirine resistance, and 2 with evidence of dolutegravir resistance substitutions. Six isolates showed genotypic and/or phenotypic resistance to rilpivirine with emergent NNRTI-resistance substitutions E138E/A (rilpivirine 1.6-fold change), M230M/L (rilpivirine 2-fold change), L100L/I, K101Q, and E138A (rilpivirine 4.1-fold change), K101K/E (rilpivirine 1.2-fold change), K101K/E, M230M/L (rilpivirine 2-fold change), and L100L/V/M, M230M/L (rilpivirine 31-fold change). In addition, 1 virologic failure subject had NNRTI‑resistance substitutions K103N and V179I at Week 88 with rilpivirine phenotypic fold change of 5.2 but had no baseline sample.

One virologic failure isolate had emergent INSTI‑resistance substitution V151V/I present post-baseline with baseline INSTI‑resistance substitutions N155N/H and G163G/R (by exploratory HIV proviral DNA archive sequencing); no integrase phenotypic data were available for this isolate at virologic failure. One other subject had the dolutegravir resistance substitution G193E at baseline and virologic failure, but no detectable phenotypic resistance (fold change = 1.02) at Week 24.

No resistance-associated substitutions were observed for the 2 subjects meeting confirmed virologic failure in the comparative current antiretroviral regimen arms at Week 48.

Treatment-Experienced, Integrase Strand Transfer Inhibitor-Experienced Subjects: VIKING-3 examined the efficacy of dolutegravir 50 mg twice daily plus optimized background therapy in subjects with prior or current virologic failure on an INSTI- (elvitegravir or raltegravir) containing regimen. Use of TIVICAY in INSTI-experienced patients should be guided by the number and type of baseline INSTI substitutions. The efficacy of TIVICAY 50 mg twice daily is reduced in patients with an INSTI-resistance Q148 substitution plus 2 or more additional INSTI-resistance substitutions, including T66A, L74I/M, E138A/K/T, G140S/A/C, Y143R/C/H, E157Q, G163S/E/K/Q, or G193E/R.

Response by Baseline Genotype

Of the 183 subjects with baseline data, 30% harbored virus with a substitution at Q148, and 33% had no primary INSTI-resistance substitutions (T66A/I/K, E92Q/V, Y143R/C/H, Q148H/R/K, and N155H) at baseline, but had historical genotypic evidence of INST-resistance substitutions, phenotypic evidence of elvitegravir or raltegravir resistance, or genotypic evidence of INSTI-resistance substitutions at screening.

Response rates by baseline genotype were analyzed in an “as-treated” analysis at Week 48 (n = 175) (Table 13). The response rate at Week 48 to dolutegravir-containing regimens was 47% (24 of 51) when Q148 substitutions were present at baseline; Q148 was always present with additional INSTI-resistance substitutions (Table 13). In addition, a diminished virologic response of 40% (6 of 15) was observed when the substitution E157Q or K was present at baseline with other INSTI-resistance substitutions but without a Q148H or R substitution.

Table 13. Response by Baseline Integrase Genotype in Subjects with Prior Experience to an Integrase Strand Transfer Inhibitor in VIKING-3
Baseline Genotype | Week 48 (<50 copies/mL) n = 175
Overall Response | 66% (116/175)
No Q148 substitutiona | 74% (92/124)
Q148H/R + G140S/A/C without additional INSTI-resistance substitutionb | 61% (17/28)
Q148H/R + ≥2 INSTI-resistance substitutionsb,c | 29% (6/21)
INSTI = integrase strand transfer inhibitor.
a Includes INSTI-resistance substitutions Y143R/C/H and N155H.
b INSTI-resistance substitutions included T66A, L74I/M, E138A/K/T, G140S/A/C, Y143R/C/H, E157Q, G163S/E/K/Q, or G193E/R. Two additional subjects had baseline genotypes of Q148Q/R plus L74L/I/M (virologic failure) and Q148R plus E138K (responder).
c The most common pathway with Q148H/R + greater than or equal to 2 INSTI-resistance substitutions had Q148+G140+E138 substitutions (n = 16).

Response by Baseline Phenotype

Response rates by baseline phenotype were analyzed in an as-treated analysis using all subjects with available baseline phenotypes through Week 48 (n = 163) (Table 14). These baseline phenotypic groups are based on subjects enrolled in VIKING-3 and are not meant to represent definitive clinical susceptibility cut points for dolutegravir. The data are provided to guide clinicians on the likelihood of virologic success based on pretreatment susceptibility to dolutegravir in INSTI-resistant patients.

Table 14. Response by Baseline Dolutegravir Phenotype (Fold-Change from Reference) in Subjects with Prior Experience to an Integrase Strand Transfer Inhibitor in VIKING-3
Baseline Dolutegravir Phenotype (Fold-Change from Reference) | Response at Week 48 (<50 copies/mL) Subset n = 163
Overall Response | 64% (104/163)
<3-fold change | 72% (83/116)
3- <10-fold change | 53% (18/34)
≥10-fold change | 23% (3/13)

Integrase Strand Transfer Inhibitor Treatment-Emergent Resistance

There were 50 subjects with virologic failure on the dolutegravir twice-daily regimen in VIKING-3 with HIV-1 RNA greater than 400 copies/mL at the failure timepoint, Week 48 or beyond, or the last timepoint on trial. Thirty-nine subjects with virologic failure had resistance data that were used in the Week 48 analysis. In the Week 48 resistance analysis 85% (33 of 39) of the subjects with virologic failure had treatment-emergent INSTI-resistance substitutions in their isolates. The most common treatment-emergent INSTI-resistance substitution was T97A. Other frequently emergent INSTI-resistance substitutions included L74M, I or V, E138K or A, G140S, Q148H, R or K, M154I, or N155H. Substitutions E92Q, Y143R or C/H, S147G, V151A, and E157E/Q each emerged in 1 to 3 subjects’ isolates. At failure, the median dolutegravir fold-change from reference was 61-fold (range: 0.75 to 209) for isolates with emergent INSTI-resistance substitutions (n = 33).

Resistance to one or more background drugs in the dolutegravir twice-daily regimen also emerged in 49% (19 of 39) of subjects in the Week 48 resistance analysis.

In VIKING-4 (ING116529), 30 subjects with current virological failure on an INSTI-containing regimen and genotypic evidence of INSTI-resistance substitutions at screening were randomized to receive either dolutegravir 50 mg twice daily or placebo with the current failing regimen for 7 days and then all subjects received open-label dolutegravir plus optimized background regimen from Day 8. Virologic responses at Week 48 by baseline genotypic and phenotypic INSTI-resistance categories and the INSTI resistance-associated substitutions that emerged on dolutegravir treatment in VIKING-4 were consistent with those seen in VIKING-3.

Cross-Resistance

Site-Directed Integrase Strand Transfer Inhibitor-Resistant Mutant HIV-1 and HIV-2 Strains: The susceptibility of dolutegravir was tested against 60 INSTI-resistant site-directed mutant HIV-1 viruses (28 with single substitutions and 32 with 2 or more substitutions) and 6 INSTI-resistant site-directed mutant HIV-2 viruses. The single INSTI-resistance substitutions T66K, I151L, and S153Y conferred a greater than 2-fold decrease in dolutegravir susceptibility (range: 2.3-fold to 3.6-fold from reference). Combinations of multiple substitutions T66K/L74M, E92Q/N155H, G140C/Q148R, G140S/Q148H, R or K, Q148R/N155H, T97A/G140S/Q148, and substitutions at E138/G140/Q148 showed a greater than 2-fold decrease in dolutegravir susceptibility (range: 2.5-fold to 21-fold from reference). In HIV-2 mutants, combinations of substitutions A153G/N155H/S163G and E92Q/T97A/N155H/S163D conferred 4-fold decreases in dolutegravir susceptibility, and E92Q/N155H and G140S/Q148R showed 8.5-fold and 17-fold decreases in dolutegravir susceptibility, respectively.

Reverse Transcriptase Inhibitor- and Protease Inhibitor-Resistant Strains: Dolutegravir demonstrated equivalent antiviral activity against 2 NNRTI-resistant, 3 NRTI-resistant, and 2 PI-resistant HIV-1 mutant clones compared with the wild-type strain.

13 NONCLINICAL TOXICOLOGY

13.1 Carcinogenesis, Mutagenesis, Impairment of Fertility

Carcinogenesis

Two-year carcinogenicity studies in mice and rats were conducted with dolutegravir. Mice were administered doses of up to 500 mg/kg, and rats were administered doses of up to 50 mg/kg. In mice, no significant increases in the incidence of drug-related neoplasms were observed at the highest doses tested, resulting in dolutegravir AUC exposures approximately 14 times higher than those in humans at the maximum recommended dose. In rats, no increases in the incidence of drug-related neoplasms were observed at the highest dose tested, resulting in dolutegravir AUC exposures 10 times and 15 times higher in males and females, respectively, than those in humans at the maximum recommended dose.

Mutagenesis

Dolutegravir was not genotoxic in the bacterial reverse mutation assay, mouse lymphoma assay, or in the in vivo rodent micronucleus assay.

Impairment of Fertility

In a study conducted in rats, there were no effects on mating or fertility with dolutegravir up to 1,000 mg/kg/day. This dose is associated with an exposure that is approximately 24 times higher than the exposure in humans at the maximum recommended dose.

14 CLINICAL STUDIES

14.1 Description of Clinical Studies

The efficacy and safety of TIVICAY or TIVICAY PD were evaluated in the studies summarized in Table 15.

Table 15. Trials Conducted with TIVICAY or TIVICAY PD in HIV-1–Infected Subjects
Population | Trial | Trial Arms | Timepoint (Week)
Adults:
Treatment-naïve | SPRING-2 (ING113086) (NCT01227824) | TIVICAY + 2 NRTIs (n = 403); Raltegravir + 2 NRTIs (n = 405) | 96
Treatment-naïve | SINGLE (ING114467) (NCT01263015) | TIVICAY + EPZICOM (n = 414); ATRIPLA (n = 419) | 144
Treatment-naïve | FLAMINGO (ING114915) (NCT01449929) | TIVICAY + NRTI BR (n = 243); Darunavir/ritonavir + NRTI BR (n = 242) | 96
Treatment-experienced, INSTI-naïve | SAILING (ING111762) (NCT01231516) | TIVICAY + BR (n = 354); Raltegravir + BR (n = 361) | 48
INSTI-experienced | VIKING-3 (ING112574); (NCT01328041) | TIVICAY + OBT (n = 183) | 48
Virologically suppressed | SWORD-1 (NCT02429791); SWORD-2 (NCT02422797) | Pooled presentation; TIVICAY + Rilpivirine (n = 513); CAR (n = 511) | 48
Pediatrics:; 4 weeks and older and weighing at least 3 kg without INSTI resistance | IMPAACT P1093 (NCT01302847) | TIVICAY or TIVICAY PD + BR (n = 75) | 24
NRTI = nucleoside reverse transcriptase inhibitor; BR = Background regimen; INSTI = integrase strand transfer inhibitor; OBT = Optimized background therapy; CAR = Current antiretroviral regimen.

14.2 Adult Subjects

Treatment-Naïve Subjects

In SPRING-2, 822 subjects were randomized and received at least 1 dose of either TIVICAY 50 mg once daily or raltegravir 400 mg twice daily, both in combination with fixed-dose dual NRTI treatment (either abacavir sulfate and lamivudine [EPZICOM] or emtricitabine/tenofovir [TRUVADA]). There were 808 subjects included in the efficacy and safety analyses. At baseline, the median age of subjects was 36 years, 13% female, 15% non-white, 11% had hepatitis B and/or C virus co-infection, 2% were CDC Class C (AIDS), 28% had HIV-1 RNA greater than 100,000 copies per mL, 48% had CD4+ cell count less than 350 cells/mm^3, and 39% received EPZICOM; these characteristics were similar between treatment groups.

In SINGLE, 833 subjects were randomized and received at least 1 dose of either TIVICAY 50 mg once daily with fixed-dose abacavir sulfate and lamivudine (EPZICOM) or fixed-dose efavirenz/emtricitabine/tenofovir (ATRIPLA). At baseline, the median age of subjects was 35 years, 16% female, 32% non-white, 7% had hepatitis C co-infection (hepatitis B virus co-infection was excluded), 4% were CDC Class C (AIDS), 32% had HIV-1 RNA greater than 100,000 copies/mL, and 53% had CD4+ cell count less than 350 cells/mm^3; these characteristics were similar between treatment groups.

Outcomes for SPRING-2 (Week 96 analysis) and SINGLE (Week 144 open-label phase analysis which followed the Week 96 double-blind phase) are provided in Table 16. Side-by-side tabulation is to simplify presentation; direct comparisons across trials should not be made due to differing trial designs.

Table 16. Virologic Outcomes of Randomized Treatment in SPRING-2 at Week 96 and SINGLE at Week 144 (Snapshot Algorithm)
 | SPRING-2 Week 96 |  | SINGLE Week 144
 | TIVICAY 50 mg Once Daily + 2 NRTIs (n = 403) | Raltegravir 400 mg Twice Daily + 2 NRTIs (n = 405) | TIVICAY 50 mg + EPZICOM Once Daily (n = 414) | ATRIPLA Once Daily (n = 419)
HIV-1 RNA <50 copies/mL | 82% | 78% | 71% | 63%
Treatment differencea | 4.9% (95% CI: -0.6%, 10.3%)b |  | 8.3% (95% CI: 2.0%, 14.6%)c
Virologic nonresponse | 5% | 10% | 10% | 7%
Data in window not <50 copies/mL | 1% | 3% | 4% | <1%
Discontinued for lack of efficacy | 2% | 3% | 3% | 3%
Discontinued for other reasons while not suppressed | <1% | 3% | 3% | 4%
Change in ART regimen | <1% | <1% | 0 | 0
No virologic data | 12% | 12% | 18% | 30%
Reasons
Discontinued study/study drug due to adverse event or deathd | 2% | 2% | 4% | 14%
Discontinued study/study drug for other reasonse | 8% | 9% | 12% | 13%
Missing data during window but on study | 2% | <1% | 2% | 3%
Proportion (%) of Subjects with HIV-1 RNA <50 copies/mL by Baseline Category
Plasma viral load (copies/mL)
≤100,000 | 84% | 83% | 73% | 64%
>100,000 | 79% | 63% | 69% | 61%
Gender
Male | 84% | 79% | 72% | 66%
Female | 70% | 68% | 69% | 48%
Race
White | 83% | 78% | 72% | 71%
African-American/African Heritage/Other | 77% | 75% | 71% | 47%
NRTI = Nucleoside reverse transcriptase inhibitor.
a Adjusted for pre-specified stratification factors.
b The primary endpoint was assessed at Week 48 and the virologic success rate was 88% in the group receiving TIVICAY and 86% in the raltegravir group, with a treatment difference of 2.6% and 95% CI of (-1.9%, 7.2%).
c The primary endpoint was assessed at Week 48 and the virologic success rate was 88% in the group receiving TIVICAY and 81% in the ATRIPLA group, with a treatment difference of 7.4% and 95% CI of (2.5%, 12.3%).
d Includes subjects who discontinued due to an adverse event or death at any time point if this resulted in no virologic data on treatment during the analysis window.
e Other includes reasons such as withdrew consent, loss to follow-up, moved, and protocol deviation.

SPRING-2: Virologic outcomes were also comparable across baseline characteristics including CD4+ cell count, age, and use of EPZICOM or TRUVADA as NRTI background regimen. The median change in CD4+ cell counts from baseline was 276 cells/mm^3 in the group receiving TIVICAY and 264 cells/mm^3 for the raltegravir group at 96 weeks.

There was no treatment-emergent resistance to dolutegravir or to the NRTI background.

SINGLE: Treatment differences were maintained across baseline characteristics including baseline viral load, CD4+ cell count, age, gender, and race.

The adjusted mean changes in CD4+ cell counts from baseline were 378 cells/mm^3 in the group receiving TIVICAY + EPZICOM and 332 cells/mm^3 for the ATRIPLA group at 144 weeks. The adjusted difference between treatment arms and 95% CI was 46.9 cells/mm^3 (15.6 cells/mm^3, 78.2 cells/mm^3) (adjusted for pre-specified stratification factors: baseline HIV-1 RNA, and baseline CD4+ cell count).

There was no treatment-emergent resistance to dolutegravir, abacavir, or lamivudine.

FLAMINGO: In FLAMINGO, 485 subjects were randomized and received at least 1 dose of either TIVICAY 50 mg once daily (n = 243) or darunavir + ritonavir 800 mg/100 mg once daily (n = 242), both in combination with investigator-selected NRTI background regimen (either fixed-dose abacavir and lamivudine [EPZICOM] or fixed-dose emtricitabine/tenofovir disoproxil fumarate [TRUVADA]). There were 484 subjects included in the efficacy and safety analyses. At baseline, the median age of subjects was 34 years, 15% female, 28% non-white, 10% had hepatitis B and/or C virus co-infection, 3% were CDC Class C (AIDS), 25% had HIV‑1 RNA greater than 100,000 copies/mL, and 35% had CD4+ cell count less than 350 cells/mm^3; these characteristics were similar between treatment groups. Overall response rates by Snapshot algorithm through Week 96 were 80% for TIVICAY and 68% for darunavir/ritonavir. The proportion of subjects who were non-responders (HIV-1 RNA greater than or equal to 50 copies per mL) at Week 96 was 8% and 12% in the arms receiving TIVICAY and darunavir + ritonavir, respectively; no virologic data were available for 12% and 21% for subjects treated with TIVICAY and darunavir + ritonavir, respectively. The adjusted overall response rate difference in proportion and 95% CI was 12.4% (4.7%, 20.2%). No treatment-emergent primary resistance substitutions were observed in either treatment group.

Treatment-Experienced, Integrase Strand Transfer Inhibitor-Naïve Subjects

In the international, multicenter, double-blind trial (SAILING), 719 HIV‑1–infected, antiretroviral treatment-experienced adults were randomized and received either TIVICAY 50 mg once daily or raltegravir 400 mg twice daily with investigator-selected background regimen consisting of up to 2 agents, including at least 1 fully active agent. There were 715 subjects included in the efficacy and safety analyses. At baseline, the median age was 43 years, 32% were female, 50% non-white, 16% had hepatitis B and/or C virus co-infection, 46% were CDC Class C (AIDS), 20% had HIV-1 RNA greater than 100,000 copies/mL, and 72% had CD4+ cell count less than 350 cells/mm^3; these characteristics were similar between treatment groups. All subjects had at least 2-class antiretroviral treatment resistance, and 49% of subjects had at least 3-class antiretroviral treatment resistance at baseline. Week 48 outcomes for SAILING are shown in Table 17.

Table 17. Virologic Outcomes of Randomized Treatment in SAILING at 48 Weeks (Snapshot Algorithm)
 | TIVICAY 50 mg Once Daily + BRa; (n = 354) | Raltegravir 400 mg Twice Daily + BRa; (n = 361)
HIV-1 RNA <50 copies/mL | 71% | 64%
Adjustedb treatment difference | 7.4% (95% CI: 0.7%, 14.2%)
Virologic nonresponse | 20% | 28%
No virologic data | 9% | 9%
Reasons
Discontinued study/study drug due to adverse event or death | 3% | 4%
Discontinued study/study drug for other reasonsc | 5% | 4%
Missing data during window but on study | 2% | 1%
Proportion (%) with HIV-1 RNA <50 copies/mL by Baseline Category
Plasma viral load (copies/mL)
≤50,000 copies/mL | 75% | 71%
>50,000 copies/mL | 62% | 47%
Background regimen
No darunavir use | 67% | 60%
Darunavir use with primary PI substitutions | 85% | 67%
Darunavir use without primary PI substitutions | 69% | 70%
Gender
Male | 70% | 66%
Female | 74% | 60%
Race
White | 75% | 71%
African-American/African Heritage/Other | 67% | 57%
a BR = Background regimen. Background regimen was restricted to less than or equal to 2 antiretroviral treatments with at least 1 fully active agent.
b Adjusted for pre-specified stratification factors.
c Other includes reasons such as withdrew consent, loss to follow-up, moved, and protocol deviation.

Treatment differences were maintained across the baseline characteristics including CD4+ cell count and age.

The mean changes in CD4+ cell counts from baseline were 162 cells/mm^3 in the group receiving TIVICAY and 153 cells/mm^3 in the raltegravir group.

Treatment-Experienced, Integrase Strand Transfer Inhibitor-Experienced Subjects

VIKING-3 examined the effect of TIVICAY 50 mg twice daily over 7 days of functional monotherapy, followed by OBT with continued treatment of TIVICAY 50 mg twice daily.

In the multicenter, open-label, single-arm VIKING-3 trial, 183 HIV‑1–infected, antiretroviral treatment-experienced adults with virological failure and current or historical evidence of raltegravir and/or elvitegravir resistance received TIVICAY 50 mg twice daily with the current failing background regimen for 7 days, then received TIVICAY with OBT from Day 8. A total of 183 subjects enrolled: 133 subjects with INSTI resistance at screening and 50 subjects with only historical evidence of resistance (and not at screening). At baseline, median age of subjects was 48 years; 23% were female, 29% non-white, and 20% had hepatitis B and/or C virus co-infection. Median baseline CD4+ cell count was 140 cells/mm^3, median duration of prior antiretroviral treatment was 13 years, and 56% were CDC Class C. Subjects showed multiple-class antiretroviral treatment resistance at baseline: 79% had greater than or equal to 2 NRTI, 75% greater than or equal to 1 NNRTI, and 71% greater than or equal to 2 PI major substitutions; 62% had non-R5 virus.

Mean reduction from baseline in HIV-1 RNA at Day 8 (primary endpoint) was 1.4 log10 (95% CI: 1.3 log10, 1.5 log10). Response at Week 48 was affected by baseline INSTI substitutions [see Microbiology (12.4)].

After the functional monotherapy phase, subjects had the opportunity to re-optimize their background regimen when possible. Week 48 virologic outcomes for VIKING-3 are shown in Table 18.

Table 18. Virologic Outcomes of Treatment of VIKING-3 at 48 Weeks (Snapshot Algorithm)
 | TIVICAY 50 mg Twice Daily + OBT; (n = 183)
HIV-1 RNA <50 copies/mL | 63%
Virologic nonresponse | 32%
No virologic data; Reasons
Discontinued study/study drug due to adverse event or death | 3%
Proportion (%) with HIV-1 RNA <50 copies/mL by Baseline Category
Gender
Male | 63%
Female | 64%
Race
White | 63%
African-American/African Heritage/Other | 64%
OBT = Optimized Background Therapy.

Subjects harboring virus with Q148 and with additional Q148-associated secondary substitutions also had a reduced response at Week 48 in a stepwise fashion [see Microbiology (12.4)].

The median change in CD4+ cell count from baseline was 80 cells/mm^3 at Week 48.

Virologically Suppressed Subjects

SWORD-1 and SWORD-2 are identical 148-week, Phase III, randomized, multicenter, parallel-group, non-inferiority trials. A total of 1,024 adult HIV-1–infected subjects who were on a stable suppressive antiretroviral regimen (containing 2 NRTIs plus either an INSTI, an NNRTI, or a PI) for at least 6 months (HIV-1 RNA less than 50 copies/mL), with no history of treatment failure and no known substitutions associated with resistance to dolutegravir or rilpivirine received treatment in the trials. Subjects were randomized 1:1 to continue their current antiretroviral regimen (n = 511) or be switched to TIVICAY 50 mg plus rilpivirine 25 mg administered once daily (n = 513). Subjects originally assigned to continue their current antiretroviral regimen and who remained virologically suppressed at Week 48 switched to TIVICAY plus rilpivirine at Week 52 (n = 477).

The primary efficacy endpoint for the SWORD trial was the proportion of subjects with plasma HIV-1 RNA less than 50 copies/mL at Week 48. The proportion of subjects with HIV-1 RNA less than 50 copies/mL at Week 48 was 95% for both treatment groups; treatment difference and 95% CI was -0.2% (-3.0%, 2.5%). The proportion of subjects with HIV‑1 RNA greater than or equal to 50 copies/mL (virologic failure) at Week 48 was 0.6% and 1.2% for the dolutegravir plus rilpivirine treatment group and the current antiretroviral regimen treatment groups, respectively; treatment difference and 95% CI was -0.6% (-1.7%, 0.6%). At Week 148 in the pooled SWORD-1 and SWORD-2 trials, 84% of subjects who received TIVICAY plus rilpivirine from study start had plasma HIV-1 RNA less than 50 copies/mL (Snapshot algorithm). In subjects who initially remained on their current antiretroviral regimen and switched to TIVICAY plus rilpivirine at Week 52, 90% had plasma HIV-1 RNA less than 50 copies/mL at Week 148 (Snapshot algorithm), which was comparable to the response rate (89%) observed at Week 100 (similar exposure duration) in subjects receiving TIVICAY plus rilpivirine from study start.

Refer to the prescribing information for JULUCA (dolutegravir and rilpivirine) tablet for complete virologic outcome information.

14.3 Pediatric Subjects

IMPAACT P1093 is an ongoing Phase I/II, multicenter, open-label trial to evaluate the pharmacokinetic parameters, safety, tolerability, and efficacy of TIVICAY or TIVICAY PD in combination treatment regimens in HIV-1–infected infants, children, and adolescents aged at least 4 weeks to 18 years. Subjects were stratified by 5 age cohorts: Cohort 1, aged 12 to less than 18 years; Cohort 2A, aged 6 to less than 12 years; Cohort 3, aged 2 to less than 6 years; Cohort 4, aged 6 months to less than 2 years; and Cohort 5, aged 4 weeks to less than 6 months. Seventy-five subjects received the recommended dose (determined by weight and age) of TIVICAY or TIVICAY PD [see Dosage and Administration (2.2, 2.3, 2.4)].

These 75 subjects had a median age of 27 months (range: 1 to 214), were 59% female, and 68% were Black or African American. At baseline, mean plasma HIV-1 RNA was 4.4 log10 copies/mL, median CD4+ cell count was 1,225 cells/mm^3 (range: 1 to 8,255), and median CD4+% was 23% (range: 0.3% to 49%). Overall, 33% had baseline plasma HIV-1 RNA greater than 50,000 copies/mL and 12% had a CDC HIV clinical classification of category C. The majority (80%) of subjects were treatment-experienced, but all were INSTI-naïve. Most subjects had previously used at least 1 NNRTI (44%) or 1 PI (76%).

Virologic outcomes from IMPAACT P1093 include subjects who received either TIVICAY tablets or TIVICAY PD tablets for oral suspension as per the dosing recommendations for their weight band and who had reached Week 24 (n = 58) or Week 48 (n = 42). At Week 24, 62% of subjects achieved HIV-1 RNA less than 50 copies/mL and 86% achieved HIV-1 RNA less than 400 copies/mL (Snapshot algorithm). The median CD4 count (percent) increase from baseline to Week 24 was 105 cells/mm^3 (5%). At Week 48, 69% of subjects achieved HIV-1 RNA less than 50 copies/mL and 79% achieved HIV-1 RNA less than 400 copies/mL (Snapshot algorithm). The median CD4 count (percent) increase from baseline to Week 48 was 141 cells/mm^3 (7%).

16 HOW SUPPLIED/STORAGE AND HANDLING

TIVICAY tablets, 10 mg, are white, round, film-coated, biconvex tablets debossed with “SV 572” on one side and “10” on the other side. Bottle of 30 tablets with child-resistant closure and containing a desiccant. NDC 49702-226-13.

Store and dispense the 10-mg tablets in the original package, protect from moisture, and keep the bottle tightly closed. Do not remove desiccant.

TIVICAY tablets, 25 mg, are pale yellow, round, film-coated, biconvex tablets debossed with “SV 572” on one side and “25” on the other side. Bottle of 30 tablets with child-resistant closure. NDC 49702-227-13.

TIVICAY tablets, 50 mg, are yellow, round, film-coated, biconvex tablets debossed with “SV 572” on one side and “50” on the other side. Bottle of 30 tablets with child-resistant closure. NDC 49702-228-13.

Store TIVICAY tablets at 25°C (77°F); excursions permitted 15° to 30°C (59° to 86°F) [See USP Controlled Room Temperature].

TIVICAY PD tablets for oral suspension, 5 mg, are white, round, strawberry cream flavored, film-coated, biconvex tablets debossed with “SV H7S” on one side and “5” on the other side. Bottle of 60 tablets with child-resistant closure containing a desiccant. Each bottle is packaged with one 30-mL dosing cup and one 10-mL oral dosing syringe with 1-mL gradations. NDC 49702-255-37.

Store TIVICAY PD tablets for oral suspension below 30°C (86°F). Store and dispense the 5-mg tablets in the original bottle, protect from moisture, and keep the bottle tightly closed. Do not remove desiccant.

17 PATIENT COUNSELING INFORMATION

Advise the patient to read the FDA-approved patient labeling (Patient Information and Instructions for Use).

Drug Interactions

TIVICAY or TIVICAY PD may interact with other drugs; therefore, advise patients to report to their healthcare provider the use of any other prescription or nonprescription medication or herbal products, including St. John’s wort [see Contraindications (4), Warnings and Precautions (5.4), Drug Interactions (7)].

Hypersensitivity Reactions

Advise patients to immediately contact their healthcare provider if they develop rash. Instruct patients to immediately stop taking TIVICAY or TIVICAY PD and other suspect agents, and seek medical attention if they develop a rash associated with any of the following symptoms, as it may be a sign of a more serious reaction such as severe hypersensitivity: fever; generally ill feeling; extreme tiredness; muscle or joint aches; blisters or peeling of the skin; oral blisters or lesions; eye inflammation; facial swelling; swelling of the eyes, lips, tongue, or mouth; breathing difficulty; and/or signs and symptoms of liver problems (e.g., yellowing of the skin or whites of the eyes, dark or tea-colored urine, pale-colored stools or bowel movements, nausea, vomiting, loss of appetite, or pain, aching, or sensitivity on the right side below the ribs) [see Warnings and Precautions (5.1)].

Hepatotoxicity

Inform patients that hepatotoxicity has been reported with dolutegravir [see Warnings and Precautions (5.2)]. Advise patients that laboratory monitoring for hepatoxicity during therapy with TIVICAY or TIVICAY PD is recommended, especially for patients with liver disease, such as hepatitis B or C.

Immune Reconstitution Syndrome

Advise patients to inform their healthcare provider immediately of any signs or symptoms of infection as inflammation from previous infection may occur soon after combination antiretroviral therapy, including when TIVICAY or TIVICAY PD is started [see Warnings and Precautions (5.4)].

Different Formulations Are Not Bioequivalent

Advise patients that TIVICAY and TIVICAY PD are not bioequivalent and are not substitutable on a milligram-per-milligram basis. Advise patients or their care provider that patients switching from one formulation to the other must adjust the dose for the new dosage formulation [see Dosage and Administration (2.2) and Warnings and Precautions (5.5)].

Pregnancy Registry

Inform patients that there is an antiretroviral pregnancy registry to monitor fetal outcomes in those exposed to TIVICAY or TIVICAY PD during pregnancy [see Use in Specific Populations (8.1)].

Lactation

Inform individuals with HIV-1 infection that the potential risks of breastfeeding include: (1) HIV-1 transmission (in HIV-1–negative infants), (2) developing viral resistance (in HIV-1–positive infants), and (3) adverse reactions in a breastfed infant similar to those seen in adults [see Use in Specific Populations (8.2)].

Administration Instructions

To avoid a dosing error from using the wrong formulation of dolutegravir, strongly advise patients and caregivers to visually inspect the tablets to verify the correct formulation each time the prescription is filled [see Dosage and Administration (2), Warnings and Precautions (5.5), How Supplied/Storage and Handling (16)].

Inform patients and caregivers that TIVICAY PD tablets for oral suspension may be swallowed whole or dispersed in drinking water and should not be chewed, cut or crushed. The amount of water needed to disperse the tablet will depend on the dose (number of tablets prescribed).

Instruct patients and caregivers that if a dose of TIVICAY or TIVICAY PD is missed, to take it as soon as they remember. Advise patients and caregivers not to double the next dose or take more than the prescribed dose [see Dosage and Administration (2)].

Storage

Instruct patients and caregivers to store the TIVICAY 10-mg tablets and TIVICAY PD 5-mg tablets for oral suspension in the original package, keep the bottle tightly closed, and protect from moisture. Do not remove desiccant [see How Supplied/Storage and Handling (16)].

TIVICAY, TIVICAY PD, EPZICOM, JULUCA, and TRIUMEQ are trademarks owned by or licensed to the ViiV Healthcare group of companies.

The other brands listed are trademarks owned by or licensed to their respective owners and are not owned by or licensed to the ViiV Healthcare group of companies. The makers of these brands are not affiliated with and do not endorse the ViiV Healthcare group of companies or its products.

Manufactured for:

ViiV Healthcare

Durham, NC 27701

©2025 ViiV Healthcare group of companies or its licensor.

TVC:20PI

PHARMACIST‑DETACH HERE AND GIVE INSTRUCTIONS TO PATIENT
_ _ _ _ _ _ _ _ _ _ _ _ _ _ _ _ _ _ _ _ _ _ _ _ _ _ _ _ _ _ _ _ _ _ _ _ _ _ _ _ _ _ _ _ _ _ _ _ _ _ _ _ _

PATIENT INFORMATION

TIVICAY (TIV-eh-kay)

(dolutegravir)

tablets

TIVICAY PD (TIV-eh-kay Pe De)

(dolutegravir)

tablets for oral suspension

What is TIVICAY and TIVICAY PD?

TIVICAY and TIVICAY PD are prescription medicines used to treat Human Immunodeficiency Virus-1 (HIV-1) infection together with:

- other HIV-1 medicines in adults who have not received HIV-1 medicines in the past or to replace their current HIV-1 medicines.
- other HIV-1 medicines in children, aged at least 4 weeks and weighing at least 6.6 pounds (3 kg), who have not received HIV-1 medicines in the past or to replace their current HIV-1 medicines when their healthcare provider determines that they meet certain requirements.

TIVICAY is used together with rilpivirine as a complete regimen to treat Human Immunodeficiency Virus-1 (HIV-1) infection in adults to replace their current HIV-1 medicines when their healthcare provider determines that they meet certain requirements.

HIV-1 is the virus that causes Acquired Immune Deficiency Syndrome (AIDS).

It is not known if TIVICAY or TIVICAY PD is safe and effective in children who are less than 4 weeks of age and weigh less than 6.6 pounds (3 kg) or in children who have received certain types of medicine for HIV-1 infection.

Do not take TIVICAY or TIVICAY PD if you:

- have ever had an allergic reaction to a medicine that contains dolutegravir.
- take dofetilide.

Before you take TIVICAY or TIVICAY PD, tell your healthcare provider about all of your medical conditions, including if you:

- have or have had liver problems, including hepatitis B or C infection.
- are pregnant or plan to become pregnant. Talk to your healthcare provider about the benefits and risks of treatment with TIVICAY or TIVICAY PD during pregnancy.

Pregnancy Registry. There is a pregnancy registry for those who take TIVICAY or TIVICAY PD during pregnancy. The purpose of this registry is to collect information about the health of you and your baby. Talk with your healthcare provider about how you can take part in this registry.

- are breastfeeding or plan to breastfeed. TIVICAY and TIVICAY PD pass to your baby in your breast milk. Talk with your healthcare provider about the following risks to your baby from breastfeeding during treatment with TIVICAY and TIVICAY PD:
  - the HIV-1 virus may pass to your baby if your baby does not have HIV-1 infection.
  - the HIV-1 virus may become harder to treat if your baby has HIV-1 infection.
  - your baby may get side effects from TIVICAY.

Tell your healthcare provider about all the medicines you take, including prescription and over-the-counter medicines, vitamins, and herbal supplements.

Some medicines interact with TIVICAY or TIVICAY PD. Keep a list of your medicines and show it to your healthcare provider and pharmacist when you get a new medicine.

- You can ask your healthcare provider or pharmacist for a list of medicines that interact with TIVICAY or TIVICAY PD.
- Do not start taking a new medicine without telling your healthcare provider. Your healthcare provider can tell you if it is safe to take TIVICAY or TIVICAY PD with other medicines.

How should I take TIVICAY or TIVICAY PD?

- Take TIVICAY or TIVICAY PD exactly as your healthcare provider tells you to take it.
- Take TIVICAY or TIVICAY PD with or without food.
- For children who cannot swallow tablets, read the Instructions for Use at the end of this patient information for detailed instructions on how to prepare a dose of TIVICAY PD tablets for oral suspension.
- TIVICAY PD may be swallowed whole or dispersed in drinking water and should not be chewed, cut, or crushed.
- TIVICAY tablets are not the same as TIVICAY PD tablets for oral suspension and cannot be substituted for each other. Check to make sure you receive the correct form of TIVICAY each time you or your child’s prescription is filled to avoid using the wrong medicine.
- Do not change your dose, switch medicines or stop taking TIVICAY or TIVICAY PD without talking with your healthcare provider first.
- If you take antacids, laxatives, or other medicines that contain aluminum, magnesium, or buffered medicines, TIVICAY or TIVICAY PD should be taken at least 2 hours before or 6 hours after you take these medicines.
- If you need to take iron or calcium supplements by mouth during treatment with TIVICAY or TIVICAY PD:
  - If you take TIVICAY with food, you may take these supplements at the same time that you take TIVICAY.
  - If you do not take TIVICAY or TIVICAY PD with food, take TIVICAY or TIVICAY PD at least 2 hours before or 6 hours after you take these supplements.
- Do not miss a dose of TIVICAY or TIVICAY PD.
- If you miss a dose of TIVICAY or TIVICAY PD, take it as soon as you remember. Do not take 2 doses at the same time or take more than your prescribed dose.
- Stay under the care of a healthcare provider during treatment with TIVICAY or TIVICAY PD.
- Do not run out of TIVICAY or TIVICAY PD. The virus in your blood may increase and the virus may become harder to treat. When your supply starts to run low, get more from your healthcare provider or pharmacy.
- If you take too much TIVICAY or TIVICAY PD, call your healthcare provider or go to the nearest hospital emergency room right away.

What are the possible side effects of TIVICAY or TIVICAY PD?

- TIVICAY or TIVICAY PD can cause serious side effects including:
- Allergic reactions. Call your healthcare provider right away if you develop a rash with TIVICAY or TIVICAY PD. Stop taking TIVICAY or TIVICAY PD and get medical help right away if you develop a rash with any of the following signs or symptoms:

- fever
- generally ill feeling
- tiredness
- muscle or joint aches
- blisters or sores in mouth

- blisters or peeling of the skin
- redness or swelling of the eyes
- swelling of the mouth, face, lips, or tongue
- problems breathing

- Liver problems. People with a history of hepatitis B or C virus may have an increased risk of developing new or worsening changes in certain liver tests during treatment with TIVICAY or TIVICAY PD. Liver problems, including liver failure, have also happened in people without a history of liver disease or other risk factors. Your healthcare provider may do blood tests to check your liver. Call your healthcare provider right away if you develop any of the following signs or symptoms of liver problems:

- your skin or the white part of your eyes turns yellow (jaundice)
- dark or “tea-colored” urine
- light-colored stools (bowel movements)

- nausea or vomiting
- loss of appetite
- pain, aching, or tenderness on the right side of your stomach area

- Changes in your immune system (Immune Reconstitution Syndrome) can happen when you start taking HIV-1 medicines. Your immune system may get stronger and begin to fight infections that have been hidden in your body for a long time. Tell your healthcare provider right away if you start having new symptoms after you start taking TIVICAY or TIVICAY PD.
- The most common side effects of TIVICAY include:

- trouble sleeping

- tiredness

- headache

These are not all the possible side effects of TIVICAY or TIVICAY PD. Call your doctor for medical advice about side effects. You may report side effects to FDA at 1‑800‑FDA‑1088.

How should I store TIVICAY or TIVICAY PD?

- Store TIVICAY 10-mg, 25-mg, and 50-mg tablets at room temperature between 68°F to 77°F (20°C to 25°C).
- Store TIVICAY 10-mg tablets in the original bottle. Keep the bottle tightly closed and protected from moisture. The bottle contains a desiccant packet to help keep your medicine dry (protect it from moisture). Do not remove the desiccant packet from the bottle.
- Store TIVICAY PD 5-mg tablets for oral suspension at room temperature below 86°F (30°C) in the original bottle. Keep the bottle tightly closed and protected from moisture. The bottle contains a desiccant packet to help keep your medicine dry (protect it from moisture). Do not remove the desiccant packet from the bottle.

Keep TIVICAY, TIVICAY PD, and all medicines out of the reach of children.

General information about the safe and effective use of TIVICAY or TIVICAY PD.

Medicines are sometimes prescribed for purposes other than those listed in a Patient Information leaflet. Do not use TIVICAY or TIVICAY PD for a condition for which it was not prescribed. Do not give TIVICAY or TIVICAY PD to other people, even if they have the same symptoms you have. It may harm them. You can ask your healthcare provider or pharmacist for information about TIVICAY that is written for health professionals.

What are the ingredients in TIVICAY and TIVICAY PD?

Active ingredient: dolutegravir.

Inactive ingredients:

TIVICAY tablets: D-mannitol, microcrystalline cellulose, povidone K29/32, sodium starch glycolate, and sodium stearyl fumarate. The tablet film‑coating contains the inactive ingredients iron oxide yellow (for the 25-mg and 50-mg tablets only), macrogol/PEG, polyvinyl alcohol-part hydrolyzed, talc, and titanium dioxide.

TIVICAY PD tablets for oral suspension: calcium sulfate dihydrate, crospovidone, mannitol, microcrystalline cellulose, povidone K29/32, silicified microcrystalline cellulose, sodium starch glycolate, strawberry cream flavor, sucralose, and sodium stearyl fumarate. The tablet film-coating contains hypromellose, polyethylene glycol, and titanium dioxide.

Manufactured for:

ViiV Healthcare

Durham, NC 27701

TIVICAY and TIVICAY PD are trademarks owned by or licensed to the ViiV Healthcare group of companies.

©2024 ViiV Healthcare group of companies or its licensor.

TVC:14PIL

For more information, go to www.TIVICAY.com or call 1-877-844-8872.

This Patient Information has been approved by the U.S. Food and Drug Administration.

Revised: 4/2024

INSTRUCTIONS FOR USE

TIVICAY PD (TIV-eh-kay Pe De)

(dolutegravir) tablets for oral suspension

5 mg

Read this Instructions for Use before giving a dose of medicine.

Follow the steps below, using clean drinking water to prepare and give a dose to an infant or a child who cannot swallow the tablets.

Important information

Always give this medicine exactly as your healthcare provider tells you. Talk to your healthcare provider if you are not sure.

Do not chew, cut, or crush the tablets.

If you forget to give a dose of medicine, give it as soon as you remember. Do not give 2 doses at the same time or give more than your healthcare provider has prescribed.

If your child does not or cannot take the full dose, call your healthcare provider.

If you give too much medicine, get emergency medical help right away.

If your child is able and prefers to swallow the tablets, then you may skip the following steps.

Your pack contains:

- A bottle containing 60 TIVICAY PD tablets for oral suspension.
- Dosing kit:
  - Cup: Use this to prepare and give the medicine to children.
  - Syringe: Use this to give the medicine to infants.

You will also need:

- Clean drinking water.

Getting Ready

Step 1. Pour water

Figure A

- Pour clean drinking water into the cup.
  The Water Volume Guide in Figure A shows the amount of water needed for the prescribed dose.
  See Figure A.

Use drinking water only.

Do not use any other drink or food to prepare the dose.

Step 2. Prepare the medicine

Figure B Figure C

- Add the prescribed number of tablet(s) to the water. See Figure B.
- Swirl the cup gently for 1 to 2 minutes to disperse the tablet(s). The medicine will become cloudy. Take care not to spill any of the medicine. See Figure C.
- Check that the medicine is ready. If there are any lumps of tablet, swirl the cup until they are gone.

If you spill any medicine, clean up the spill.

Throw away the rest of the prepared medicine and make a new dose.

You must give the dose of medicine within 30 minutes of preparing the dose. If it has been more than 30 minutes, wash away all the dose in the cup using water and prepare a new dose of medicine.

Giving the medicine

Step 3. Give the medicine

Figure D

- Make sure that the child is upright. Give all the prepared medicine to the child. See Figure D.
- Add another 5 mL of drinking water to the cup, swirl, and give it all to the child.
- Repeat if any medicine remains in the cup to make sure the child gets the full dose.

Figure E Figure F

- Place the tip of the syringe into the prepared medicine and draw up all the medicine into the syringe by pulling up on the plunger. See Figure E.
- Place the tip of the syringe against the inside of the infant’s cheek. Gently push down the plunger to give the dose slowly. See Figure F.
- Add another 5 mL of drinking water to the cup and swirl. Draw up the remaining medicine into the syringe and give it all to the infant.
- Repeat if any medicine remains in the syringe to make sure the infant gets the full dose.

Allow time for the medicine to be swallowed.

Cleaning

Step 4. Clean the dosing items

Figure G Figure H

- Wash the cup with water. See Figure G.
- Pull the plunger out of the syringe and wash the syringe parts separately in water. Allow parts to dry completely before reassembling and storing. See Figure H.
- All parts will need to be clean before preparing the next dose.

Storage Information

Store TIVICAY PD tablets for oral suspension at room temperature below 86°F (30°C) in the original bottle. Keep the bottle tightly closed and protect from moisture. The bottle contains a desiccant packet to help keep your medicine dry (protect it from moisture). Do not remove the desiccant packet from the bottle.

Keep TIVICAY PD and all medicines out of the reach of children.

Disposal Information

When all the tablets in the bottle have been taken or are no longer needed, throw away the bottle, cup, and syringe. Dispose of them using your local household waste guidelines.

You will get a new cup and syringe in your next pack.

Manufactured for:

ViiV Healthcare

Durham, NC 27701

Trademarks are owned by or licensed to the ViiV Healthcare group of companies.

©2024 ViiV Healthcare group of companies or its licensor.

TVC: 3IFU

This Instructions for Use has been approved by the U.S. Food and Drug Administration.

Revised: 4/2024

PACKAGE LABEL

PRINCIPAL DISPLAY PANEL

NDC 49702-255-37

Tivicay PD

(dolutegravir) Tablets for Oral Suspension

5 mg

Rx Only

Tivicay and Tivicay PD are not interchangeable.

Each tablet contains 5 mg of dolutegravir equivalent to 5.26 mg of dolutegravir sodium.

Do not chew, cut, or crush tablet for oral suspension.

Do not accept if security seal is missing or broken.

See prescribing information for dosage information.

Contents:

- 1 Bottle of 60 tablets
- 1 Oral dosing syringe
- 1 Dosing cup
- Prescribing Information
- Instruction for Use

60 tablets

©2024 ViiV Healthcare group of companies or its licensor.

Made in Japan

Rev. 1/2024

62000000091728

PACKAGE LABEL

PRINCIPAL DISPLAY PANEL

NDC 49702-226-13

Tivicay

(dolutegravir)

Tablets

10 mg

Rx Only

Each film-coated tablet contains dolutegravir sodium equivalent to 10 mg of dolutegravir.

30 Tablets

Keep out of reach of children.

Store in original package at controlled room temperature of 25°C (77°F); excursions permitted to 15° to 30°C (59° to 86°F) [See USP].

Keep bottle tightly closed; protect from moisture. Do not remove desiccant.

Do not accept if membrane seal under cap is missing or broken.

See prescribing information for dosage information.

Manufactured for:

ViiV Healthcare

Durham, NC 27701

by:

GlaxoSmithKline

Durham, NC 27701

Made in Japan

Rev. 2/23

62000000085469

PACKAGE LABEL

PRINCIPAL DISPLAY PANEL

NDC 49702-227-13

Tivicay

(dolutegravir)

Tablets

25 mg

Rx Only

Each film-coated tablet contains dolutegravir sodium equivalent to 25 mg of dolutegravir.

30 Tablets

Keep out of reach of children.

Store at controlled room temperature of 25°C (77°F); excursions permitted to 15° to 30°C (59° to 86°F) [See USP].

Do not accept if membrane seal under cap is missing or broken.

See prescribing information for dosage information.

Manufactured for:

ViiV Healthcare

Durham, NC 27701

by:

GlaxoSmithKline

Durham, NC 27701

Made in Japan

Rev. 2/23

62000000085470

PACKAGE LABEL

PRINCIPAL DISPLAY PANEL

NDC 49702-228-13

Tivicay

(dolutegravir)

Tablets

50 mg

Rx Only

Each film-coated tablet contains dolutegravir sodium equivalent to 50 mg of dolutegravir.

30 Tablets

Keep out of reach of children.

Store at controlled room temperature of 25°C (77°F); excursions permitted to 15° to 30°C (59° to 86°F) [see USP].

Do not accept if membrane seal under cap is missing or broken.

See prescribing information for dosage information.

Manufactured for:

ViiV Healthcare

Durham, NC 27701

by:

GlaxoSmithKline

Durham, NC 27701

Made in Japan

Rev. 2/23

62000000085468